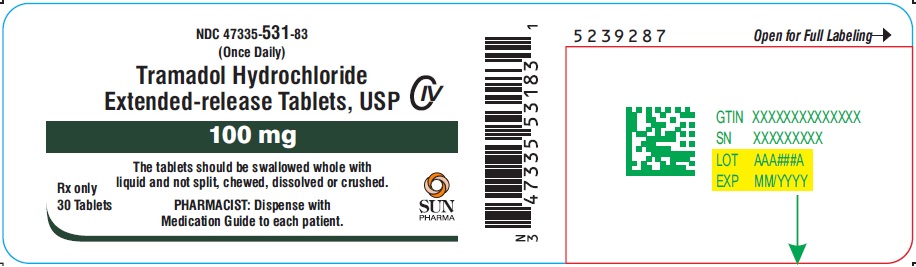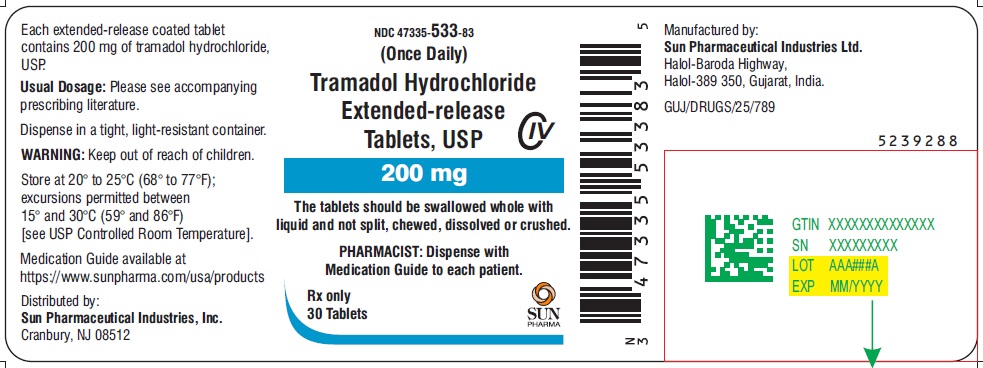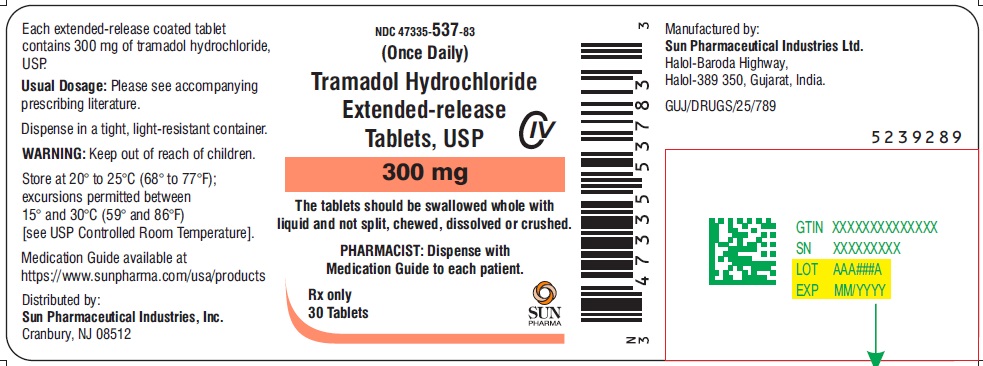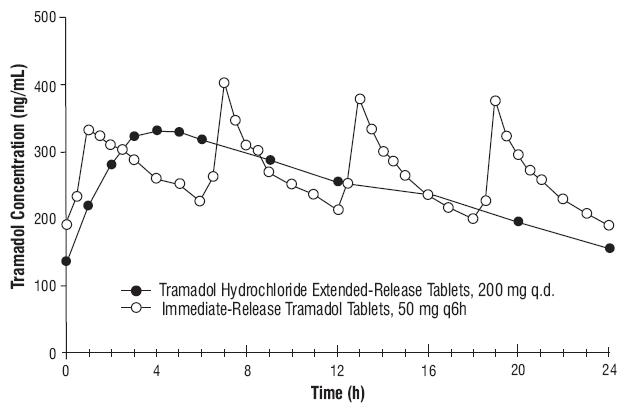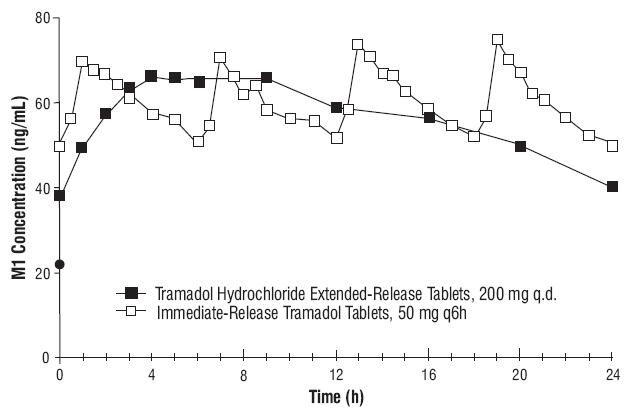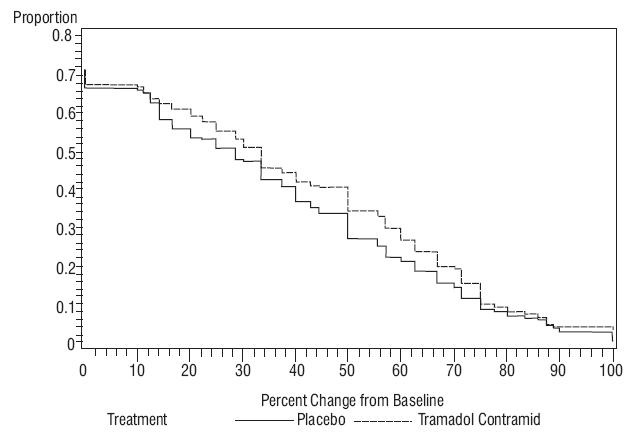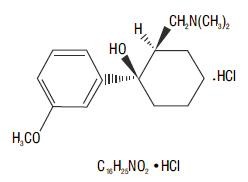 DRUG LABEL: TRAMADOL HYDROCHLORIDE
NDC: 47335-531 | Form: TABLET, EXTENDED RELEASE
Manufacturer: Sun Pharmaceutical Industries, Inc.
Category: prescription | Type: Human Prescription Drug Label
Date: 20251205
DEA Schedule: CIV

ACTIVE INGREDIENTS: TRAMADOL HYDROCHLORIDE 100 mg/1 1
INACTIVE INGREDIENTS: STARCH, CORN; HYPROMELLOSE 2910 (5 MPA.S); MANNITOL; MAGNESIUM STEARATE; CELLULOSE ACETATE; POLYETHYLENE GLYCOL, UNSPECIFIED; SHELLAC; BUTYL ALCOHOL; PROPYLENE GLYCOL; AMMONIA; FERROSOFERRIC OXIDE

Tramadol Hydrochloride Extended-Release Tablets, USP C-IV
Rx Only

WARNING: SERIOUS AND LIFE-THREATENING RISKS FROM USE OF TRAMADOL HYDROCHLORIDE EXTENDED-RELEASE TABLETS

Addiction, Abuse, and Misuse

Because the use of tramadol hydrochloride extended-release tablets exposes patients and other users to the risks of opioid addiction, abuse, and misuse, which can lead to overdose and death, assess each patient’s risk prior to prescribing and reassess all patients regularly for the development of these behaviors and conditions [see Warnings].

Life-Threatening Respiratory Depression

Serious, life-threatening, or fatal respiratory depression may occur with use of tramadol hydrochloride extended-release tablets, especially during initiation or following a dose increase. To reduce the risk of respiratory depression, proper dosing and titration of tramadol hydrochloride extended-release tablets are essential [see Warnings]. Instruct patients to swallow tramadol hydrochloride extended-release tablets whole to avoid exposure to a potentially fatal dose of tramadol.

Accidental Ingestion

Accidental ingestion of even one dose of tramadol hydrochloride extended-release tablets, especially by children, can result in a fatal overdose of tramadol [see Warnings].

Risks From Concomitant Use With Benzodiazepines Or Other CNS Depressants

Concomitant use of opioids with benzodiazepines or other central nervous system (CNS) depressants, including alcohol, may result in profound sedation, respiratory depression, coma, and death. Reserve concomitant prescribing of tramadol hydrochloride extended-release tablets and benzodiazepines or other CNS depressants for use in patients for whom alternative treatment options are inadequate [see Warnings, Precautions; Drug Interactions].

Neonatal Opioid Withdrawal Syndrome (NOWS)

Advise pregnant women using opioids for an extended period of time of the risk of Neonatal Opioid Withdrawal Syndrome, which may be life-threatening if not recognized and treated. Ensure that management by neonatology experts will be available at delivery [see Warnings].

Opioid Analgesic Risk Evaluation and Mitigation Strategy (REMS):

Healthcare providers are strongly encouraged to complete a REMS-compliant education program and to counsel patients and caregivers on serious risks, safe use, and the importance of reading the Medication Guide with each prescription [see Warnings].

Ultra-Rapid Metabolism of Tramadol and Other Risk Factors for Life-Threatening Respiratory Depression in Children

Life-threatening respiratory depression and death have occurred in children who received tramadol. Some of the reported cases followed tonsillectomy and/or adenoidectomy; in at least one case, the child had evidence of being an ultra-rapid metabolizer of tramadol due to a CYP2D6 polymorphism [see WARNINGS]. Tramadol hydrochloride extended-release tablets are contraindicated in children younger than 12 years of age and in children younger than 18 years of age following tonsillectomy and/or adenoidectomy [see CONTRAINDICATIONS]. Avoid the use of tramadol hydrochloride extended-release tablets in adolescents 12 to 18 years of age who have other risk factors that may increase their sensitivity to the respiratory depressant effects of tramadol [see WARNINGS].

Interactions with Drugs Affecting Cytochrome P450 Isoenzymes

The effects of concomitant use or discontinuation of cytochrome P450 3A4 inducers, 3A4 inhibitors, or 2D6 inhibitors with tramadol hydrochloride are complex. Use of cytochrome P450 3A4 inducers, 3A4 inhibitors, or 2D6 inhibitors with Tramadol Extended-Release Tablets requires careful consideration of the effects on the parent drug, tramadol, and the active metabolite, M1 [see WARNINGS, PRECAUTIONS; Drug Interactions].

DESCRIPTION

Tramadol hydrochloride extended-release tablets, USP are an opioid agonist composed of a matrix delivery system with extended-release characteristics. The chemical name for tramadol hydrochloride, USP is (±)cis-2-[(dimethylamino) methyl]-1-(3 methoxyphenyl) cyclohexanol hydrochloride. Its structural formula is:

The molecular weight of tramadol hydrochloride, USP is 299.8. Tramadol hydrochloride, USP is a white crystalline powder that is freely soluble in water and ethanol. Tramadol hydrochloride extended-release tablets, USP are for oral administration and contain 100 mg, 200 mg or 300 mg of tramadol hydrochloride, USP. The tablets are white in color. The inactive ingredients in the tablet are pregelatinized maize starch, hypromellose, mannitol, magnesium stearate, cellulose acetate and polyethylene glycol.

Imprinting ink contains shellac glaze, iron oxide black, N-butyl alcohol, propylene glycol and ammonium hydroxide.

Meets USP dissolution test 4.

CLINICAL PHARMACOLOGY

Mechanism of Action

Tramadol hydrochloride extended-release tablets, contain tramadol, an opioid agonist inhibitor of norepinenphrine and serotonin re-uptake. Although the mode of action of tramadol is not completely understood, the analgesic effect of tramadol is believed to be due to binding to μ-opioid receptors and weak inhibition of reuptake of norepinephrine and serotonin.

Opioid activity of tramadol is due to both low affinity binding of the parent compound and higher affinity binding of the O-demethylated metabolite (M1) to mu-opioid receptors. In animal models, M1 is up to 6 times more potent than tramadol in producing analgesia and 200 times more potent in mu-opioid binding. Tramadol-induced analgesia is only partially antagonized by the opiate antagonist naloxone in several animal tests. The relative contribution of both tramadol and M1 to human analgesia is dependent upon the plasma concentrations of each compound.

Tramadol has been shown to inhibit reuptake of norepinephrine and serotonin in vitro, as have some other opioid analgesics. These mechanisms may contribute independently to the overall analgesic profile of tramadol.

Apart from analgesia, tramadol hydrochloride administration may produce various symptoms (including dizziness, somnolence, nausea, constipation, sweating and pruritus) similar to that of other opioids. In contrast to morphine, tramadol has not been shown to cause histamine release. At therapeutic doses, tramadol has no effect on heart rate, left-ventricular function or cardiac index. Orthostatic hypotension has been observed.

Pharmacodynamics

Effects on the Central Nervous System

Tramadol produces respiratory depression by direct action on brain stem respiratory centers. The respiratory depression involves a reduction in the responsiveness of the brain stem respiratory centers to both increases in carbon dioxide tension and electrical stimulation.

Tramadol causes miosis, even in total darkness. Pinpoint pupils are a sign of opioid overdose but are not pathognomonic (e.g., pontine lesions of hemorrhagic or ischemic origins may produce similar findings). Marked mydriasis rather than miosis may be seen due to hypoxia in overdose situations.

Effects on the Gastrointestinal Tract and Other Smooth Muscle

Tramadol causes a reduction in motility associated with an increase in smooth muscle tone in the antrum of the stomach and duodenum. Digestion of food in the small intestine is delayed and propulsive contractions are decreased. Propulsive peristaltic waves in the colon are decreased, while tone may be increased to the point of spasm, resulting in constipation. Other opioid-induced effects may include a reduction in biliary and pancreatic secretions, spasm of sphincter of Oddi, transient elevations in serum amylase, and opioid-induced esophageal dysfunction (OIED).

Effects on the Cardiovascular System

Tramadol produces peripheral vasodilation, which may result in orthostatic hypotension or syncope. Manifestations of histamine release and/or peripheral vasodilation may include pruritus, flushing, red eyes, sweating, and/or orthostatic hypotension.

Effects on the Endocrine System

Opioids inhibit the secretion of adrenocorticotropic hormone (ACTH), cortisol, and luteinizing hormone (LH) in humans [see ADVERSE REACTIONS]. They also stimulate prolactin, growth hormone (GH) secretion, and pancreatic secretion of insulin and glucagon.

Use of opioids for an extended period of time may influence the hypothalamic-pituitary-gonadal axis, leading to androgen deficiency that may manifest as low libido, impotence, erectile dysfunction, amenorrhea, or infertility. The causal role of opioids in the clinical syndrome of hypogonadism is unknown because the various medical, physical, lifestyle, and psychological stressors that may influence gonadal hormone levels have not been adequately controlled for in studies conducted to date [see ADVERSE REACTIONS].

Effects on the Immune System

Opioids have been shown to have a variety of effects on components of the immune system. The clinical significance of these findings is unknown. Overall, the effects of opioids appear to be modestly immunosuppressive.

Concentration–Efficacy Relationships

The minimum effective analgesic concentration will vary widely among patients, especially among patients who have been previously treated with extended-release agonist opioids. The minimum effective analgesic concentration of tramadol for any individual patient may increase over time due to an increase in pain, the development of a new pain syndrome, and/or the development of analgesic tolerance [see DOSAGE and ADMINISTRATION].

Concentration–Adverse Reaction Relationships

There is a relationship between increasing tramadol plasma concentration and increasing frequency of dose-related opioid adverse reactions such as nausea, vomiting, CNS effects, and respiratory depression. In opioid-tolerant patients, the situation may be altered by the development of tolerance to opioid-related adverse reactions [see DOSAGE and ADMINISTRATION].

Pharmacokinetics

Tramadol hydrochloride extended-release tablets are formulated as a racemate and both tramadol and M1 are detected in the circulation.

The pharmacokinetics of tramadol and M1 are dose-proportional over a 100 to 300 mg dose range in healthy subjects.

Absorption

The median time to peak plasma concentrations of tramadol and M1 after multiple-dose administration of a tramadol hydrochloride extended-release tablet 200 mg to healthy subjects are attained at about 4 h and 5 h, respectively (Table 1 and Figure 1).

The pharmacokinetic parameter values of a tramadol hydrochloride extended-release tablet 200 mg administered once daily and tramadol immediate-release 50 mg administered every six hours are provided in Table 1. The relative bioavailability of a 200 mg tramadol hydrochloride extended-release tablet compared to a 50 mg immediate-release tablet dosed every six hours was approximately 95% in healthy subjects.

Table 1. Mean (%CV) Steady-State Pharmacokinetic Parameter Values (n=26).
Pharmacokinetic Parameter | Tramadol |  | M1 Metabolite
Pharmacokinetic Parameter | Tramadol Hydrochloride Extended-Release 200 mg Tablet Once-Daily | Immediate- Release Tramadol 50 mg Tablet Every 6 Hours | Tramadol Hydrochloride Extended-Release 200 mg Tablet Once-Daily | Immediate- Release Tramadol 50 mg Tablet Every 6 Hours
AUC0-24 (ng·h/mL) | 5991 (22) | 6399 (28) | 1361 (27) | 1438 (23)
Cmax (ng/mL) | 345 (21) | 423 (23) | 71 (27) | 79 (22)
Cmin (ng/mL) | 157 (31) | 190 (34) | 41 (30) | 50 (29)
Tmax (hr) [Tmax is presented as Median (Range)] | 4.0 (3.0 to 9.0) | 1.0 (1.0 to 3.0) | 5.0 (3.0 to 20) | 1.5 (1.0 to 3.0)
Fluctuation (%) | 77 (26) | 91 (22) | 53 (29) | 49 (26)

Steady-state plasma concentrations are reached within approximately 48 hours.
Figure 1. Mean Tramadol Plasma Concentrations at Steady State Following Five Days of Oral Administration of A Tramadol Hydrochloride Extended-Release Tablet 200 mg Once Daily and Immediate-Release Tramadol 50 mg Every 6 Hours.
Figure 2. Mean M1 Plasma Concentrations at Steady State Following Five Days of Oral Administration of A Tramadol Hydrochloride Extended-Release Tablet 200 mg Once Daily and Immediate-Release Tramadol 50 mg Every 6 Hours
Food Effect

Coadministration with a high fat meal did not significantly affect AUC (overall exposure to tramadol); however, Cmax (peak plasma concentration) increased 67% following a single 300 mg tablet administration and 54% following a single 200 mg tablet administration. Tramadol hydrochloride extended-release tablets were administered without regard to food in all clinical trials.

Distribution

The volume of distribution of tramadol is 2.6 and 2.9 L/kg in males and females, respectively, following a 100 mg intravenous dose. The binding of tramadol to human plasma proteins is approximately 20%. Protein binding also appears to be independent of concentration up to 10 mcg/mL. Saturation of plasma protein binding occurs only at concentrations outside the clinically relevant range.

Elimination

After single administration of tramadol hydrochloride extended-release tablets, the mean terminal plasma elimination half-lives of racemic tramadol and racemic M1 are 6.5 ± 1.5 and 7.5 ± 1.4 hours, respectively.

Metabolism

Tramadol is extensively metabolized after oral administration. The major metabolic pathways appear to be N- and O-demethylation and glucuronidation or sulfation in the liver. N-demethylation is mediated by CYP3A4 and CYP2B6. One metabolite (O-desmethyltramadol, denoted M1) is pharmacologically active in animal models. Formation of M1 is dependent on CYP2D6 and as such is subject to inhibition and polymorphism, which may affect the therapeutic response [see PRECAUTIONS - Drug Interactions].

Excretion

Approximately 30% of the dose is excreted in the urine as unchanged drug, whereas 60% of the dose is excreted as metabolites. The remainder is excreted either as unidentified or as unextractable metabolites.

Special Populations

Hepatic Impairment

The metabolism of tramadol and M1 is reduced in patients with advanced cirrhosis of the liver, resulting in both a larger area under the concentration time curve (AUC) for tramadol and longer mean tramadol and M1 elimination half-lives (13 hours for tramadol and 19 hours for M1) after the administration of tramadol immediate-release tablets. Tramadol hydrochloride extended-release tablets have not been studied in patients with hepatic impairment. The limited availability of dose strengths and once daily dosing of tramadol hydrochloride extended-release tablets do not permit the dosing flexibility required for safe use in patients with hepatic impairment. Therefore, tramadol hydrochloride extended-release tablets should not be used in patients with hepatic impairment [see WARNINGS, Use in Renal and Hepatic Disease and DOSAGE and ADMINISTRATION].

Renal Impairment

Impaired renal function results in a decreased rate and extent of excretion of tramadol and its active metabolite, M1 in patients taking an immediate-release formulation of tramadol. Tramadol hydrochloride extended-release tablets have not been studied in patients with renal impairment. The limited availability of dose strengths and once daily dosing of tramadol hydrochloride extended-release tablets do not permit the dosing flexibility required for safe use in patients with severe renal impairment. Therefore, tramadol hydrochloride extended-release tablets should not be used in patients with severe renal impairment (creatinine clearance less than 30 mL/min) [see WARNINGS, Use in Renal and Hepatic Disease and DOSAGE and ADMINISTRATION]. The total amount of tramadol and M1 removed during a 4-hour dialysis period is less than 7% of the administered dose.

Geriatric Patients

Healthy elderly subjects aged 65 to 75 years administered an immediate-release formulation of tramadol, have plasma concentrations and elimination half-lives comparable to those observed in healthy subjects less than 65 years of age. In subjects over 75 years, mean maximum plasma concentrations are elevated (208 vs. 162 ng/mL) and the mean elimination half-life is prolonged (7 vs. 6 hours) compared to subjects 65 to 75 years of age. Adjustment of the daily dose is recommended for patients older than 75 years [see DOSAGE and ADMINISTRATION].

Sex

Following a 100 mg IV dose of tramadol, plasma clearance was 6.4 mL/min/kg in males and 5.7 mL/min/kg in females. Following a single oral dose of immediate-release tramadol, and after adjusting for body weight, females had a 12% higher peak tramadol concentration and a 35% higher area under the concentration-time curve compared to males. The clinical significance of this difference is unknown.

Drug Interaction Studies

Potential for Tramadol to Affect Other Drugs

In vitro studies indicate that tramadol is unlikely to inhibit the CYP3A4-mediated metabolism of other drugs when tramadol is administered concomitantly at therapeutic doses. Tramadol does not appear to induce its own metabolism in humans, since observed maximal plasma concentrations after multiple oral doses are higher than expected based on single-dose data.

Poor/Extensive Metabolizers, CYP2D6

The formation of the active metabolite of tramadol, M1, is mediated by CYP2D6, a polymorphic enzyme. Approximately 7% of the population has reduced activity of CYP2D6. These individuals are "poor metabolizers" of debrisoquine, dextromethorphan and tricyclic antidepressants, among other drugs. In studies in healthy subjects administered immediate-release tramadol products, concentrations of tramadol were approximately 20% higher in "poor metabolizers" versus “extensive metabolizers”, while M1 concentrations were 40% lower.

CYP2D6 Inhibitors

In vitro drug interaction studies in human liver microsomes indicate that concomitant administration with inhibitors of CYP2D6 such as (fluoxetine paroxetine, and amitriptyline could result in some inhibition of the metabolism of tramadol.

Quinidine

Quinidine is a selective inhibitor of CYP2D6, so that concomitant administration of quinidine and tramadol hydrochloride extended-release tablets may result in increased concentrations of tramadol and reduced concentrations of M1. The clinical consequences of these findings are unknown [see PRECAUTIONS]. In vitro drug interaction studies in human liver microsomes indicate that tramadol has no effect on quinidine metabolism.

CYP3A4 Inhibitors and Inducers

Tramadol is also metabolized by CYP3A4. Administration of CYP3A4 inhibitors such as ketoconazole and erythromycin, or inducers, such as rifampin and St. John’s Wort, with tramadol hydrochloride extended-release tablets may affect the metabolism of tramadol leading to altered tramadol exposure [see PRECAUTIONS].

Cimetidine

Concomitant administration of tramadol immediate-release tablets with cimetidine, a weak CYP3A4 inhibitor, does not result in clinically significant changes in tramadol pharmacokinetics. No alteration of the tramadol hydrochloride extended-release tablets dosage regimen with cimetidine is recommended.

Carbamazepine
Carbamazepine, a CYP3A4 inducer, increases tramadol metabolism. Patients taking carbamazepine may have a significantly reduced analgesic effect of tramadol. Concomitant administration of tramadol hydrochloride extended-release tablets and carbamazepine is not recommended [see PRECAUTIONS].

CLINICAL STUDIES

Tramadol hydrochloride extended-release tablets were studied in four 12-week, randomized, double-blind, controlled studies in patients with moderate to severe pain due to osteoarthritis. Efficacy was demonstrated in one double-blind, placebo-controlled, randomized withdrawal design study. In this study, patients who experienced a reduction of pain and were able to tolerate tramadol hydrochloride extended-release tablets during an open-label titration period, were then randomized to tramadol hydrochloride extended-release tablets or to placebo for 12 weeks. Sixty-five percent of patients were able to successfully titrate onto tramadol hydrochloride extended-release tablets. After a washout, patients randomized to tramadol hydrochloride extended-release tablets were titrated to 200 mg or 300 mg of tramadol hydrochloride extended-release tablets based on tolerability and remained on that dose for the following 12-week period. Approximately 24% of patients discontinued during the randomized period of the study, with more patients discontinuing from the tramadol hydrochloride extended-release tablets arm than the placebo arm due to adverse events (10% vs. 5%, respectively) and more patients discontinuing from the placebo arm than the tramadol hydrochloride extended-release tablets arm due to lack of efficacy (10% vs. 8%, respectively). Patients treated with tramadol hydrochloride extended-release tablets demonstrated a greater improvement in pain intensity, measured on an 11-point numerical rating scale, at the end of treatment compared to patients randomized to placebo. Figure 3 shows the fraction of patients achieving various degree of improvement in pain from baseline to the end of treatment (week 12). The figure is cumulative, so that patients whose change from baseline is, for example, 50%, are also included at every level of improvement below 50%. Patients who did not complete the study were assigned 0% improvement.

Figure 3. Proportion of Patients Achieving Various Levels of Pain Relief as Measured by 12-Week Pain Intensity.

INDICATIONS AND USAGE

Tramadol hydrochloride extended-release tablets are indicated for the management of severe and persistent pain that requires an opioid analgesic and that cannot be adequately treated with alternative options, including immediate-release opioids.

Limitations of Use

• Because of the risks of addiction, abuse, misuse, overdose, and death, which can occur at any dosage or duration and persist over the course of therapy [see Warnings], reserve opioid analgesics, including tramadol hydrochloride extended-release tablets, for use in patients for whom alternative treatment options are ineffective, not tolerated, or would be otherwise inadequate to provide sufficient management of pain.

• Tramadol hydrochloride extended-release tablets are not indicated as an as-needed (prn) analgesic.

CONTRAINDICATIONS

Tramadol hydrochloride extended-release tablets are contraindicated for:

- all children younger than 12 years of age [see WARNINGS].
- postoperative management in children younger than 18 years of age following tonsillectomy and/or adenoidectomy [see WARNINGS].

Tramadol hydrochloride extended-release tablets are also contraindicated in patients with:

- Significant respiratory depression [see WARNINGS]
- Acute or severe bronchial asthma in an unmonitored setting or in the absence of resuscitative equipment [see WARNINGS]
- Known or suspected gastrointestinal obstruction, including paralytic ileus [see WARNINGS]
- Hypersensitivity to tramadol (e.g., anaphylaxis) [see ADVERSE REACTIONS]
- Concurrent use of monoamine oxidase inhibitors (MAOIs) or use within the last 14 days [see PRECAUTIONS; Drug Interactions]

WARNINGS

Addiction, Abuse, and Misuse

Tramadol hydrochloride extended-release tablets contain tramadol, a Schedule IV controlled substance. As an opioid, tramadol hydrochloride extended-release tablets expose users to the risks of addiction, abuse, and misuse [see DRUG ABUSE and DEPENDENCE].

Although the risk of addiction in any individual is unknown, it can occur in patients appropriately prescribed tramadol hydrochloride extended-release tablets. Addiction can occur at recommended dosages and if the drug is misused or abused. The risk of opioid-related overdose or overdose-related death is increased with higher opioid doses, and this risk persists over the course of therapy. In postmarketing studies, addiction, abuse, misuse, and fatal and non-fatal opioid overdose were observed in patients with long-term opioid use [see ADVERSE REACTIONS; Postmarketing Experience].

Assess each patient’s risk for opioid addiction, abuse, or misuse prior to prescribing tramadol hydrochloride extended-release tablets, and reassess all patients receiving tramadol hydrochloride extended-release tablets for the development of these behaviors or conditions. Risks are increased in patients with a personal or family history of substance abuse (including drug or alcohol abuse or addiction) or mental illness (e.g., major depression). The potential for these risks should not, however, prevent the proper management of pain in any given patient. Patients at increased risk may be prescribed opioids such as tramadol hydrochloride extended-release tablets, but use in such patients necessitates intensive counseling about the risks and proper use of tramadol hydrochloride extended-release tablets along with frequent reevaluation for signs of addiction, abuse, and misuse. Consider recommending or prescribing an opioid overdose reversal agent [see WARNINGS; Life-Threatening Respiratory Depression, DOSAGE and ADMINISTRATION; Patient Access to Naloxone for the Emergency Treatment of Opioid Overdose].

Abuse or misuse of tramadol hydrochloride extended-release tablets by cutting, breaking, chewing, crushing, snorting, or injecting the dissolved product will result in the uncontrolled delivery of tramadol and can result in overdose and death [see OVERDOSAGE].

Opioids are sought for nonmedical use and are subject to diversion from legitimate prescribed use. Consider these risks when prescribing or dispensing tramadol hydrochloride extended-release tablets. Strategies to reduce these risks include prescribing the drug in the smallest appropriate quantity and advising the patient on careful storage of the drug during the course of treatment and proper disposal of unused drug. Contact local state professional licensing board or statecontrolled substances authority for information on how to prevent and detect abuse or diversion of this product.

Life-Threatening Respiratory Depression

Serious, life-threatening, or fatal respiratory depression has been reported with the use of opioids, even when used as recommended. Respiratory depression, if not immediately recognized and treated, may lead to respiratory arrest and death. Management of respiratory depression may include close observation, supportive measures, and use of opioid overdose reversal agents, depending on the patient’s clinical status [see OVERDOSAGE]. Carbon dioxide (CO2) retention from opioid-induced respiratory depression can exacerbate the sedating effects of opioids.

While serious, life-threatening, or fatal respiratory depression can occur at any time during the use of tramadol hydrochloride extended-release tablets, the risk is greatest during the initiation of therapy or following a dosage increase.

To reduce the risk of respiratory depression, proper dosing and titration of tramadol hydrochloride extended-release tablets are essential [see DOSAGE and ADMINISTRATION]. Overestimating the tramadol hydrochloride extended-release tablets dosage when converting patients from another opioid product can result in a fatal overdose with the first dose.

Accidental ingestion of even one dose of tramadol hydrochloride extended-release tablets, especially by children, can result in respiratory depression and death due to an overdose of tramadol.

Educate patients and caregivers on how to recognize respiratory depression and emphasize the importance of calling 911 or getting emergency medical help right away in the event of a known or suspected overdose [see PRECAUTIONS; Information for Patients].

Opioids can cause sleep-related breathing disorders including central sleep apnea (CSA) and sleep-related hypoxemia. Opioid use increases the risk of CSA in a dose-dependent fashion. In patients who present with CSA, consider decreasing the opioid dosage using best practices for opioid taper [see DOSAGE and ADMINISTRATION].

Patient Access to an Opioid Overdose Reversal Agent for the Emergency Treatment of Opioid Overdose
Inform patients and caregivers about opioid overdose reversal agents (e.g., naloxone, nalmefene). Discuss the importance of having access to an opioid overdose reversal agent, especially if the patient has risk factors for overdose (e.g., concomitant use of CNS depressants, a history of opioid use disorder, or prior opioid overdose) or if there are household members (including children) or other close contacts at risk for accidental ingestion or opioid overdose. The presence of risk factors for overdose should not prevent the management of pain in any patient [see WARNINGS].

Discuss the options for obtaining an opioid overdose reversal agent (e.g., prescription, over-the-counter, or as part of a community-based program).

There are important differences among the opioid overdose reversal agents, such as route of administration, product strength, approved patient age range, and pharmacokinetics. Be familiar with these differences, as outlined in the approved labeling for those products, prior to recommending or prescribing such an agent.

Educate patients and caregivers on how to recognize respiratory depression, and how to use an opioid overdose reversal agent for them emergency treatment of opioid overdose. Emphasize the importance of calling 911 or getting emergency medical help, even if an opioid overdose reversal agent is administered [see WARNINGS, DOSAGE AND ADMINISTRATION, and OVERDOSAGE].

Risks from Concomitant Use with Benzodiazepines or Other CNS Depressants

Profound sedation, respiratory depression, coma, and death may result from the concomitant use of tramadol hydrochloride extended-release tablets with benzodiazepines and/or other CNS depressants, including alcohol (e.g., non-benzodiazepine sedatives/hypnotics, anxiolytics, tranquilizers, muscle relaxants, general anesthetics, antipsychotics, gabapentinoids [gabapentin or pregabalin], and other opioids, alcohol). Because of these risks, reserve concomitant prescribing of these drugs for use in patients for whom alternative treatment options are inadequate.

Observational studies have demonstrated that concomitant use of opioid analgesics and benzodiazepines increases the risk of drug-related mortality compared to use of opioid analgesics alone. Because of similar pharmacological properties, it is reasonable to expect similar risk with the concomitant use of other CNS depressant drugs with opioid analgesics [see PRECAUTIONS; Drug Interactions].

If the decision is made to prescribe a benzodiazepine or other CNS depressant concomitantly with an opioid analgesic, prescribe the lowest effective dosages and minimum durations of concomitant use. In patients already receiving an opioid analgesic, prescribe a lower initial dose of the benzodiazepine or other CNS depressant than indicated in the absence of an opioid, and titrate based on clinical response. If an opioid analgesic is initiated in a patient already taking a benzodiazepine or other CNS depressant, prescribe a lower initial dose of the opioid analgesic, and titrate based on clinical response. Inform patients and caregivers of this potential interaction, educate them on the signs and symptoms of respiratory depression (including sedation).

If concomitant use is warranted, consider recommending or prescribing an opioid overdose reversal agent [see WARNINGS; Life-Threatening Respiratory Depression, DOSAGE and ADMINISTRATION; Patient Access to Naloxone for the Emergency Treatment of Opioid Overdose].

Advise both patients and caregivers about the risks of respiratory depression and sedation when tramadol hydrochloride extended-release tablets are used with benzodiazepines or other CNS depressants (including alcohol and illicit drugs). Advise patients not to drive or operate heavy machinery until the effects of concomitant use of the benzodiazepine or other CNS depressant have been determined. Screen patients for risk of substance use disorders, including opioid abuse and misuse, and warn them of the risk for overdose and death associated with the use of additional CNS depressants including alcohol and illicit drugs [see PRECAUTIONS; Information for Patients, Drug Interactions].

Neonatal Opioid Withdrawal Syndrome

Use of tramadol hydrochloride extended-release tablets for an extended period of time during pregnancy can result in withdrawal in the neonate. Neonatal opioid withdrawal syndrome, unlike opioid withdrawal syndrome in adults, may be life-threatening if not recognized and treated, and requires management according to protocols developed by neonatology experts. Observe newborns for signs of neonatal opioid withdrawal syndrome and manage accordingly. Advise pregnant women using opioids for an extended period of time of the risk of neonatal opioid withdrawal syndrome and ensure that appropriate treatment will be available [see PRECAUTIONS, Information for Patients, Pregnancy].

Risk Evaluation and Mitigation Strategy (REMS)

To ensure that the benefits of opioid analgesics outweigh the risks of addiction, abuse, and misuse, the Food and Drug Administration (FDA) has required a Risk Evaluation and Mitigation Strategy (REMS) for these products. Under the requirements of the REMS, drug companies with approved opioid analgesic products must make REMS-compliant education programs available to healthcare providers. Healthcare providers are strongly encouraged to do all of the following:

- Complete a REMS-compliant education program offered by an accredited provider of continuing education (CE) or another education program that includes all the elements of the FDA Education Blueprint for Health Care Providers Involved in the Management or Support of Patients with Pain.
- Discuss the safe use, serious risks, and proper storage and disposal of opioid analgesics with patients and/or their caregivers every time these medicines are prescribed. The Patient Counseling Guide (PCG) can be obtained at this link: www.fda.gov/OpioidAnalgesicREMSPCG.
- Emphasize to patients and their caregivers the importance of reading the Medication Guide that they will receive from their pharmacist every time an opioid analgesic is dispensed to them.
- Consider using other tools to improve patient, household, and community safety, such as patient-prescriber agreements that reinforce patient-prescriber responsibilities.

To obtain further information on the opioid analgesic REMS and for a list of accredited REMS CME/CE, call 800-503-0784, or log on to www.opioidanalgesicrems.com. The FDA Blueprint can be found at www.fda.gov/OpioidAnalgesicREMSBlueprint.

Ultra-Rapid Metabolism and Other Risk Factors for Life-threatening Respiratory Depression in Children

Life-threatening respiratory depression and death have occurred in children who received tramadol. Tramadol and codeine are subject to variability in metabolism based upon CYP2D6 genotype (described below), which can lead to increased exposure to an active metabolite. Based upon postmarketing reports with tramadol or with codeine, children younger than 12 years of age may be more susceptible to the respiratory depressant effects of tramadol. Furthermore, children with obstructive sleep apnea who are treated with opioids for post-tonsillectomy and/or adenoidectomy pain may be particularly sensitive to their respiratory depressant effect. Because of the risk of life-threatening respiratory depression and death:

- Tramadol hydrochloride extended-release tablets are contraindicated for all children younger than 12 years of age [see CONTRAINDICATIONS].
- Tramadol hydrochloride extended-release tablets are contraindicated for post-operative management in pediatric patients younger than 18 years of age following tonsillectomy and/or adenoidectomy [see CONTRAINDICATIONS].
- Avoid the use of tramadol hydrochloride extended-release tablets in adolescents 12 to 18 years of age who have other risk factors that may increase their sensitivity to the respiratory depressant effects of tramadol unless the benefits outweigh the risks. Risk factors include conditions associated with hypoventilation, such as postoperative status, obstructive sleep apnea, obesity, severe pulmonary disease, neuromuscular disease, and concomitant use of other medications that cause respiratory depression.
- As with adults, when prescribing opioids for adolescents, healthcare providers should choose the lowest effective dose for the shortest period of time and inform patients and caregivers about these risks and the signs of opioid overdose [see PRECAUTIONS/Pediatric Use, OVERDOSAGE].

Risks of Interactions with Drugs Affecting Cytochrome P450 Isoenzymes

The effects of concomitant use or discontinuation of cytochrome P450 3A4 inducers, 3A4 inhibitors, or 2D6 inhibitors on levels of tramadol and M1 from tramadol hydrochloride extended-release tablets are complex. Use of cytochrome P450 3A4 inducers, 3A4 inhibitors, or 2D6 inhibitors with tramadol hydrochloride extended-release tablets require careful consideration of the effects on the parent drug, tramadol which is a weak serotonin and norepinephrine reuptake inhibitor and μ-opioid agonist, and the active metabolite, M1, which is more potent than tramadol in μ-opioid receptor binding [see PRECAUTIONS; Drug Interactions].

Risks of Concomitant Use or Discontinuation of Cytochrome P450 2D6 Inhibitors

The concomitant use of tramadol hydrochloride extended-release tablets with all cytochrome P450 2D6 inhibitors (e.g., amiodarone, quinidine) may result in an increase in tramadol plasma levels and a decrease in the levels of the active metabolite, M1. A decrease in M1 exposure in patients who have developed physical dependence to tramadol, may result in signs and symptoms of opioid withdrawal and reduced efficacy. The effect of increased tramadol levels may be an increased risk for serious adverse events including seizures and serotonin syndrome.

Discontinuation of a concomitantly used cytochrome P450 2D6 inhibitor may result in a decrease in tramadol plasma levels and an increase in active metabolite M1 levels, which could increase or prolong adverse reactions related to opioid toxicity and may cause potentially fatal respiratory depression.

Evaluate patients receiving tramadol hydrochloride extended-release tablets and any CYP2D6 inhibitor at frequent intervals for the risk of serious adverse events including seizures and serotonin syndrome, signs and symptoms that may reflect opioid toxicity, and opioid withdrawal when tramadol hydrochloride extended-release tablets are used in conjunction with inhibitors of CYP2D6 [see PRECAUTIONS; Drug Interactions].

Cytochrome P450 3A4 Interaction

The concomitant use of tramadol hydrochloride extended-release tablets with cytochrome P450 3A4 inhibitors, such as macrolide antibiotics (e.g., erythromycin), azole-antifungal agents (e.g., ketoconazole), and protease inhibitors (e.g., ritonavir) or discontinuation of a cytochrome P450 3A4 inducer such as rifampin, carbamazepine, and phenytoin, may result in an increase in tramadol plasma concentrations, which could increase or prolong adverse reactions, increase the risk for serious adverse events including seizures and serotonin syndrome, and may cause potentially fatal respiratory depression.

The concomitant use of tramadol hydrochloride extended-release tablets with all cytochrome P450 3A4 inducers or discontinuation of a cytochrome P450 3A4 inhibitor may result in lower tramadol levels. This may be associated with a decrease in efficacy, and in some patients, may result in signs and symptoms of opioid withdrawal.

Follow patients receiving tramadol hydrochloride extended-release tablets and any CYP3A4 inhibitor or inducer for the risk for serious adverse events including seizures and serotonin syndrome, signs and symptoms that may reflect opioid toxicity and opioid withdrawal when tramadol hydrochloride extended-release tablets are used in conjunction with inhibitors and inducers of CYP3A4 [see PRECAUTIONS; Drug Interactions].

CYP2D6 Genetic Variability: Ultra-Rapid Metabolizer

Some individuals may be ultra-rapid metabolizers because of a specific CYP2D6 genotype (e.g., gene duplications denoted as *1/*1xN or *1/*2xN). The prevalence of this CYP2D6 phenotype varies widely and has been estimated at 1 to 10% for Whites (European, North American), 3 to 4% for Blacks (African Americans), 1 to 2% for East Asians (Chinese, Japanese, Korean), and may be greater than 10% in certain racial/ethnic groups (i.e., Oceanian, Northern African, Middle Eastern, Ashkenazi Jews, Puerto Rican). These individuals convert tramadol into its active metabolite, O-desmethyltramadol (M1), more rapidly and completely than other people. This rapid conversion results in higher than expected serum M1 levels. Even at labeled dosage regimens, individuals who are ultra-rapid metabolizers may have life-threatening or fatal respiratory depression or experience signs of overdose (such as extreme sleepiness, confusion, or shallow breathing) [see OVERDOSAGE]. Therefore, individuals who are ultra-rapid metabolizers should not use tramadol hydrochloride extended-release tablets.

Opioid-Induced Hyperalgesia and Allodynia

Opioid-Induced Hyperalgesia (OIH) occurs when an opioid analgesic paradoxically causes an increase in pain, or an increase in sensitivity to pain. This condition differs from tolerance, which is the need for increasing doses of opioids to maintain a defined effect [see Dependence]. Symptoms of OIH include (but may not be limited to) increased levels of pain upon opioid dosage increase, decreased levels of pain upon opioid dosage decrease, or pain from ordinarily non-painful stimuli (allodynia). These symptoms may suggest OIH only if there is no evidence of underlying disease progression, opioid tolerance, opioid withdrawal, or addictive behavior.

Cases of OIH have been reported, both with short-term and longer-term use of opioid analgesics. Though the mechanism of OIH is not fully understood, multiple biochemical pathways have been implicated. Medical literature suggests a strong biologic plausibility between opioid analgesics and OIH and allodynia. If a patient is suspected to be experiencing OIH, carefully consider appropriately decreasing the dose of the current opioid analgesic or opioid rotation (safely switching the patient to a different opioid moiety) [see Dosage and Administration, Warnings].

Nursing Mothers

Tramadol is subject to the same polymorphic metabolism as codeine, with ultra-rapid metabolizers of CYP2D6 substrates being potentially exposed to life-threatening levels of the active metabolite O-desmethyltramadol (M1). At least one death was reported in a nursing infant who was exposed to high levels of morphine in breast milk because the mother was an ultra-rapid metabolizer of codeine. A baby nursing from an ultra-rapid metabolizer mother taking tramadol hydrochloride extended-release tablets could potentially be exposed to high levels of M1, and experience life-threatening respiratory depression. For this reason, breastfeeding is not recommended during treatment with tramadol hydrochloride extended-release tablets (see PRECAUTIONS/Nursing Mothers).

Serotonin Syndrome Risk

Cases of serotonin syndrome, a potentially life-threatening condition, have been reported during concomitant use of tramadol hydrochloride extended-release tablets with serotonergic drugs. Serotonergic drugs include selective serotonin reuptake inhibitors (SSRIs), serotonin and norepinephrine reuptake inhibitors (SNRIs), tricyclic antidepressants (TCAs), triptans, 5-HT3 receptor antagonists, drugs that affect the serotonergic neurotransmitter system (e.g., mirtazapine, trazodone, tramadol), certain muscle relaxants (i.e., cyclobenzaprine, metaxalone), and drugs that impair metabolism of serotonin (including MAO inhibitors, both those intended to treat psychiatric disorders and also others, such as linezolid and intravenous methylene blue) [see PRECAUTIONS; Drug Interactions]. This may occur within the recommended dosage range.

Serotonin syndrome symptoms may include mental status changes (e.g., agitation, hallucinations, coma), autonomic instability (e.g., tachycardia, labile blood pressure, hyperthermia), neuromuscular aberrations (e.g., hyperreflexia, incoordination, rigidity), and/or gastrointestinal symptoms (e.g., nausea, vomiting, diarrhea). The onset of symptoms generally occurs within several hours to a few days of concomitant use, but may occur later than that. Discontinue tramadol hydrochloride extended-release tablets if serotonin syndrome is suspected.

Increased Risk of Seizures

Seizures have been reported in patients receiving tramadol hydrochloride within the recommended dosage range. Spontaneous postmarketing reports indicate that seizure risk is increased with doses above the recommended range.

Concomitant use of tramadol hydrochloride increases the seizure risk in patients taking [see PRECAUTIONS; Drug Interactions]:

- Selective serotonin reuptake inhibitors (SSRI antidepressants or anorectics),
- Tricyclic antidepressants (TCAs), and other tricyclic compounds (e.g., cyclobenzaprine, promethazine, etc.),
- Other opioids.
- Tramadol hydrochloride extended-release tablets Monoamine Oxidase (MAO) inhibitors [see WARNINGS; Use with MAO Inhibitors and Serotonin Re-uptake Inhibitors and PRECAUTIONS; Drug Interactions],
- Neuroleptics, or
- Other drugs that reduce the seizure threshold.

Risk of seizures may also increase in patients with epilepsy, those with a history of seizures, or in patients with a recognized risk for seizure (such as head trauma, certain metabolic disorders, alcohol and drug withdrawal and CNS infections).

In tramadol overdose, administration of an opioid overdose reversal agent (e.g., naloxone or nalmefene) may increase the risk of seizures.

Suicide Risk

- Do not prescribe tramadol hydrochloride extended-release tablets for patients who are suicidal or addiction-prone. Consideration should be given to the use of non-narcotic analgesics in patients who are suicidal or depressed [see DRUG ABUSE and DEPENDENCE].
- Prescribe tramadol hydrochloride extended-release tablets with caution for patients with history of misuse and/or are currently taking CNS-active drugs including tranquilizers or antidepressant drugs, or alcohol in excess, and patients who suffer from emotional disturbance or depression [see PRECAUTIONS; Drug Interactions].

Tell your patients not to exceed the recommended dose and to limit their intake of alcohol [see DOSAGE and ADMINISTRATION and WARNINGS].

Life-Threatening Respiratory Depression in Patients with Chronic Pulmonary Disease or in Elderly, Cachectic, or Debilitated Patients

The use of tramadol hydrochloride extended-release tablets in patients with acute or severe bronchial asthma in an unmonitored setting or in the absence of resuscitative equipment is contraindicated.

Patients with Chronic Pulmonary Disease: Tramadol hydrochloride extended-release tablets-treated patients with significant chronic obstructive pulmonary disease or cor pulmonale, and those with a substantially decreased respiratory reserve, hypoxia, hypercapnia, or preexisting respiratory depression are at increased risk of decreased respiratory drive including apnea, even at recommended dosages of tramadol hydrochloride extended-release tablets [see WARNINGS; Respiratory Depression].

Elderly, Cachectic, or Debilitated Patients: Life-threatening respiratory depression is more likely to occur in elderly, cachectic, or debilitated patients because they may have altered pharmacokinetics, including clearance, compared to younger, healthier patients [see WARNINGS; Respiratory Depression].

Regularly evaluate patients, particularly when initiating and titrating tramadol hydrochloride extended-release tablets and when tramadol hydrochloride extended-release tablets are given concomitantly with other drugs that depress respiration [see Warnings; Respiratory Depression]. Alternatively, consider the use of non-opioid analgesics in these patients.

Adrenal Insufficiency

Cases of adrenal insufficiency have been reported with opioid use, more often following greater than one 1 month of use. Presentation of adrenal insufficiency may include non-specific symptoms and signs including nausea, vomiting, anorexia, fatigue, weakness, dizziness, and low blood pressure. If adrenal insufficiency is suspected, confirm the diagnosis with diagnostic testing as soon as possible. If adrenal insufficiency is diagnosed, treat with physiologic replacement doses of corticosteroids. Wean the patient off of the opioid to allow adrenal function to recover and continue corticosteroid treatment until adrenal function recovers. Other opioids may be tried as some cases reported use of a different opioid without recurrence of adrenal insufficiency. The information available does not identify any particular opioids as being more likely to be associated with adrenal insufficiency.

Severe Hypotension

Tramadol hydrochloride extended-release tablets may cause severe hypotension including hypotension and syncope in ambulatory patients. There is increased risk in patients whose ability to maintain blood pressure has already been compromised by a reduced blood volume or concurrent administration of certain CNS depressant drugs (e.g., phenothiazines or general anesthetics) [see PRECAUTIONS; Drug Interactions]. Regularly evaluate these patients for signs of hypotension after initiating or titrating the dosage of tramadol hydrochloride extended-release tablets. In patients with circulatory shock tramadol hydrochloride extended-release tablets may cause vasodilatation that can further reduce cardiac output and blood pressure. Avoid the use of tramadol hydrochloride extended-release tablets with circulatory shock.

Risks of Use in Patients with Increased Intracranial Pressure, Brain Tumors, Head Injury, or Impaired Consciousness

In patients who may be susceptible to the intracranial effects of CO2 retention (e.g., those with evidence of increased intracranial pressure or brain tumors), tramadol hydrochloride extended-release tablets may reduce respiratory drive, and the resultant CO2 retention can further increase intracranial pressure. Monitor such patients for signs of sedation and respiratory depression, particularly when initiating therapy with tramadol hydrochloride extended-release tablets.

Opioids may also obscure the clinical course in a patient with a head injury. Avoid the use of tramadol hydrochloride extended-release tablets in patients with impaired consciousness or coma.

Risks of Gastrointestinal Complications

Tramadol hydrochloride extended-release tablets are contraindicated in patients with known or suspected gastrointestinal obstruction, including paralytic ileus.

The tramadol in tramadol hydrochloride extended-release tablets may cause spasm of the sphincter of Oddi. Opioids may cause increases in serum amylase. Regularly evaluate patients with biliary tract disease, including acute pancreatitis, for worsening symptoms.

Cases of opioid-induced esophageal dysfunction (OIED) have been reported in patients taking opioids. The risk of OIED may increase as the dose and/or duration of opioids increases. Regularly evaluate patients for signs and symptoms of OIED (e.g., dysphagia, regurgitation, non-cardiac chest pain), and if necessary, adjust opioid therapy as clinically appropriate [see CLINICAL PHARMACOLOGY; Pharmacodynamics].

Anaphylaxis and Other Hypersensitivity Reactions

Serious and rarely fatal hypersensitive reactions have been reported in patients receiving therapy with tramadol. When these events do occur it is often following the first dose. Other reported hypersensitivity reactions include pruritus, hives, bronchospasm, angioedema, toxic epidermal necrolysis and Stevens-Johnson syndrome. Patients with a history of hypersensitivity reactions to tramadol and other opioids may be at increased risk and therefore should not receive tramadol hydrochloride extended-release tablets. If anaphylaxis or other hypersensitivity occurs, stop administration of tramadol hydrochloride extended-release tablets immediately, discontinue tramadol hydrochloride extended-release tablets permanently, and do not rechallenge with any formulation of tramadol. Advise patients to seek immediate medical attention if they experience any symptoms of a hypersensitivity reaction [see CONTRAINDICATIONS and PRECAUTIONS; Information for Patients].

Withdrawal

Do not rapidly reduce or abruptly discontinue tramadol hydrochloride extended-release tablets in a patient physically dependent on opioids. When discontinuing tramadol hydrochloride extended-release tablets in a physically dependent patient, gradually taper the dosage. Rapid tapering of tramadol hydrochloride extended-release tablets in a patient physically dependent on opioids may lead to a withdrawal syndrome and return of pain [see DOSAGE and ADMINISTRATION, DRUG ABUSE and DEPENDENCE].

Additionally, avoid the use of mixed agonist/antagonist (e.g., pentazocine, nalbuphine, and butorphanol) or partial agonist (e.g., buprenorphine) analgesics in patients who are receiving a full opioid agonist analgesic, including tramadol hydrochloride extended-release tablets. In these patients, mixed agonist/antagonist and partial agonist analgesics may reduce the analgesic effect and/or precipitate withdrawal symptoms [see Drug Interactions].

Risks of Driving and Operating Machinery

Tramadol hydrochloride extended-release tablets may impair the mental or physical abilities needed to perform potentially hazardous activities such as driving a car or operating machinery. Warn patients not to drive or operate dangerous machinery unless they are tolerant to the effects of tramadol hydrochloride extended-release tablets and know how they will react to the medication [see PRECAUTIONS; Information for Patients].

PRECAUTIONS

Use in Renal and Hepatic Disease

Impaired renal function results in a decreased rate and extent of excretion of tramadol and its active metabolite, M1 in patients taking an immediate-release formulation of tramadol. Tramadol hydrochloride extended-release tablets have not been studied in patients with renal impairment. The limited availability of dose strengths and once daily dosing of tramadol hydrochloride extended-release tablets do not permit the dosing flexibility required for safe use in patients with renal impairment. Therefore, tramadol hydrochloride extended-release tablets should not be used in patients with severe renal impairment [see CLINICAL PHARMACOLOGY and DOSAGE and ADMINISTRATION].

The metabolism of tramadol and M1 is reduced in patients with advanced cirrhosis of the liver. Tramadol hydrochloride extended-release tablets have not been studied in patients with hepatic impairment. The limited availability of dose strengths and once daily dosing of tramadol hydrochloride extended-release tablets do not permit the dosing flexibility required for safe use in patients with hepatic impairment. Therefore, tramadol hydrochloride extended-release tablets should not be used in patients with hepatic impairment [see CLINICAL PHARMACOLOGY and DOSAGE and ADMINISTRATION].

Information for Patients/Caregivers

Advise the patient to read the FDA-approved patient labeling (Medication Guide).

Storage and Disposal

Because of the risks associated with accidental ingestion, misuse, and abuse, advise patients to store tramadol hydrochloride extended-release tablets securely, out of sight and reach of children, and in a location not accessible by others, including visitors to the home [see WARNINGS, DRUG ABUSE and DEPENDENCE]. Inform patients that leaving tramadol hydrochloride extended-release tablets unsecured can pose a deadly risk to others in the home.

Advise patients and caregivers that when medicines are no longer needed, they should be disposed of promptly. Inform patients that medicine take-back options are the preferred way to safely dispose of most types of unneeded medicines. If no take back programs or DEA-registered collectors are available, instruct patients to dispose of tramadol hydrochloride extended-release tablets by following these four steps:

- Mix tramadol hydrochloride extended-release tablets (do not crush) with an unpalatable substance such as dirt, cat litter, or used coffee grounds;
- Place the mixture in a container such as a sealed plastic bag;
- Throw the container in the household trash;
- Remove all personal information on the prescription label of the empty bottle

Inform patients that they can visit www.fda.gov/drugdisposal for additional information on disposal of unused medicines.

Addiction, Abuse, and Misuse

Inform patients that the use of tramadol hydrochloride extended-release tablets, even when taken as recommended, can result in addiction, abuse, and misuse, which can lead to overdose and death [see WARNINGS]. Instruct patients not to share tramadol hydrochloride extended-release tablets with others and to take steps to protect tramadol hydrochloride extended-release tablets from theft or misuse.

Life-Threatening Respiratory Depression

Inform patients of the risk of life-threatening respiratory depression, including information that the risk is greatest when starting tramadol hydrochloride extended-release tablets or when the dosage is increased, and that it can occur even at recommended dosages.

Educate patients and caregivers on how to recognize respiratory depression and emphasize the importance of calling 911 or getting emergency medical help right away in the event of a known or suspected overdose [see WARNINGS; Life Threatening Respiratory Depression].

Accidental Ingestion

Inform patients that accidental ingestion, especially by children, may result in respiratory depression or death [see WARNINGS].

Interactions with Benzodiazepines or Other CNS Depressants

Inform patients and caregivers that potentially fatal additive effects may occur if tramadol hydrochloride extended-release tablets are used with benzodiazepines or other CNS depressants, including alcohol (e.g., non-benzodiazepine sedative/hypnotics, anxiolytics, tranquilizers, muscle relaxants, general anesthetics, antipsychotics, gabapentinoids [gabapentin or pregabalin], and other opioids), and not to use these concomitantly unless supervised by a healthcare provider [see WARNINGS and PRECAUTIONS; Drug Interactions].

Patient Access to an Opioid Overdose Reversal Agent for the Emergency Treatment of Opioid Overdose
Inform patients and caregivers about opioid overdose reversal agents (e.g., naloxone, nalmefene). Discuss the importance of having access to an opioid overdose reversal agent, especially if the patient has risk factors for overdose (e.g., concomitant use of CNS depressants, a history of opioid use disorder, or prior opioid overdose) or if there are household members (including children) or other close contacts at risk for accidental ingestion or opioid overdose.

Discuss with the patient the options for obtaining an opioid overdose reversal agent (e.g., prescription, over-the-counter, or as part of a community-based program) [see WARNINGS, DOSAGE AND ADMINISTRATION].

Educate patients and caregivers on how to recognize the signs and symptoms of an overdose.

Explain to patients and caregivers that effects of opioid overdose reversal agents like naloxone and nalmefene are temporary, and that they must call 911 or get emergency medical help right away in all cases of known or suspected opioid overdose, even if an opioid overdose reversal agent is administered [see OVERDOSAGE].

Advise patients and caregivers:
• how to treat with the overdose reversal agent in the event of an opioid overdose.
• to tell family and friends about their opioid overdose reversal agent, and to keep it in a place where family and friends can access it in an emergency.
• to read the Patient Information (or other educational material) that will come with their opioid overdose reversal agent. Emphasize the importance of doing this before an opioid emergency happens, so the patient and caregiver will know what to do.

Ultra-Rapid Metabolism of Tramadol and Other Risk Factors for Life-threatening Respiratory Depression in Children

Advise caregivers that tramadol hydrochloride extended-release tablets are contraindicated in all children younger than 12 years of age and in children younger than 18 years of age following tonsillectomy and/or adenoidectomy. Advise caregivers of children ages 12 to 18 years of age receiving tramadol hydrochloride extended-release tablets to monitor for signs of respiratory depression [see WARNINGS].

Hyperalgesia and Allodynia

Inform patients and caregivers not to increase opioid dosage without first consulting a clinician. Advise patients to seek medical attention if they experience symptoms of hyperalgesia, including worsening pain, increased sensitivity to pain, or new pain [see Warnings; Adverse Reactions].

Serotonin Syndrome

Inform patients that opioids could cause a rare but potentially life-threatening condition resulting from concomitant administration of serotonergic drugs. Warn patients of the symptoms of serotonin syndrome and to seek medical attention right away if symptoms develop. Instruct patients to inform their healthcare provider if they are taking, or plan to take serotonergic medications [see WARNINGS].

Seizures

Inform patients that tramadol hydrochloride extended-release tablets may cause seizures with concomitant use of serotonergic agents (including SSRIs, SNRIs, and triptans) or drugs that significantly reduce the metabolic clearance of tramadol [see WARNINGS].

MAOI Interaction

Inform patients not to take tramadol hydrochloride extended-release tablets while using any drugs that inhibit monoamine oxidase. Patients should not start MAOIs while taking tramadol hydrochloride extended-release tablets [see PRECAUTIONS; Drug Interactions].

Important Administration Instructions

Instruct patients how to properly take tramadol hydrochloride extended-release tablets, including the following:

- Tramadol hydrochloride extended-release tablets are designed to work properly only if swallowed intact. Taking cut, broken, chewed, crushed, or dissolved tramadol hydrochloride extended-release tablets can result in a fatal overdose [see DOSAGE and ADMINISTRATION].
- Advise patients not to exceed the single-dose and 24-hour dose limit and the time interval between doses, since exceeding these recommendations can result in respiratory depression, seizures, hepatic toxicity, and death. [see DOSAGE and ADMINISTRATION].
- Do not discontinue tramadol hydrochloride extended-release tablets without first discussing the need for a tapering regimen with the prescriber [see DOSAGE and ADMINISTRATION].

Important Discontinuation Instructions

In order to avoid developing withdrawal symptoms, instruct patients not to discontinue tramadol hydrochloride extended-release tablets without first discussing a tapering plan with the prescriber [see DOSAGE and ADMINISTRATION].

Driving or Operating Heavy Machinery

Inform patients that tramadol hydrochloride extended-release tablets may impair the ability to perform potentially hazardous activities such as driving a car or operating heavy machinery. Advise patients not to perform such tasks until they know how they will react to the medication [see WARNINGS].

Constipation

Advise patients of the potential for severe constipation, including management instructions and when to seek medical attention [see ADVERSE REACTIONS, CLINICAL PHARMACOLOGY].

Adrenal Insufficiency

Inform patients that opioids could cause adrenal insufficiency, a potentially life-threatening condition. Adrenal insufficiency may present with non-specific symptoms and signs such as nausea, vomiting, anorexia, fatigue, weakness, dizziness, and low blood pressure. Advise patients to seek medical attention if they experience a constellation of these symptoms [see WARNINGS].

Hypotension

Inform patients that tramadol hydrochloride extended-release tablets may cause orthostatic hypotension and syncope. Instruct patients how to recognize symptoms of low blood pressure and how to reduce the risk of serious consequences should hypotension occur (e.g., sit or lie down, carefully rise from a sitting or lying position) [see WARNINGS].

Anaphylaxis

Inform patients that anaphylaxis has been reported with ingredients contained in tramadol hydrochloride extended-release tablets. Advise patients how to recognize such a reaction and when to seek medical attention [see CONTRAINDICATIONS, ADVERSE REACTIONS].

Pregnancy

Neonatal Opioid Withdrawal Syndrome

Inform female patients of reproductive potential that use of tramadol hydrochloride extended-release tablets for an extended period of time during pregnancy can result in neonatal opioid withdrawal syndrome, which may be life-threatening if not recognized and treated [see WARNINGS, PRECAUTIONS; Pregnancy].

Embryo-Fetal Toxicity

Inform female patients of reproductive potential that tramadol hydrochloride extended-release tablets can cause fetal harm and to inform their healthcare provider of a known or suspected pregnancy [see PRECAUTIONS; Pregnancy].

Lactation

Advise women that breastfeeding is not recommended during treatment with tramadol hydrochloride extended-release tablets [see PRECAUTIONS; Nursing Mothers].

Infertility

Inform patients that use of opioids for an extended period of time may cause reduced fertility. It is not known whether these effects on fertility are reversible [see ADVERSE REACTIONS].

Drug Interactions

Inhibitors of CYP2D6

The concomitant use of tramadol hydrochloride extended-release tablets and CYP2D6 inhibitors such as quinidine, fluoxetine, paroxetine and bupropion may result in an increase in the plasma concentration of tramadol and a decrease in the plasma concentration of M1, particularly when an inhibitor is added after a stable dose of tramadol hydrochloride extended-release tablets is achieved. Since M1 is a more potent μ-opioid agonist, decreased M1 exposure could result in decreased therapeutic effects, and may result in signs and symptoms of opioid withdrawal in patients who had developed physical dependence to tramadol. Increased tramadol exposure can result in increased or prolonged therapeutic effects and increased risk for serious adverse events including seizures and serotonin syndrome.

After stopping a CYP2D6 inhibitor, as the effects of the inhibitor decline, the tramadol plasma concentration will decrease and the M1 plasma concentration will increase which could increase or prolong therapeutic effects but also increase adverse reactions related to opioid toxicity, and may cause potentially fatal respiratory depression [see CLINICAL PHARMACOLOGY].

If concomitant use of a CYP2D6 inhibitor is necessary, follow patients closely for adverse reactions including opioid withdrawal, seizures and serotonin syndrome.

If a CYP2D6 inhibitor is discontinued, consider lowering tramadol hydrochloride extended-release tablets dosage until stable drug effects are achieved. Evaluate patients at frequent intervals for adverse events including respiratory depression and sedation.

Inhibitors of CYP3A4

The concomitant use of tramadol hydrochloride extended-release tablets and CYP3A4 inhibitors such as macrolide antibiotics (e.g., erythromycin), azole-antifungal agents (e.g. ketoconazole), protease inhibitors (e.g., ritonavir) can increase the plasma concentration of tramadol and may result in a greater amount of metabolism via CYP2D6 and greater levels of M1. Follow patients closely for increased risk of serious adverse events including seizures and serotonin syndrome, and adverse reactions related to opioid toxicity including potentially fatal respiratory depression, particularly when an inhibitor is added after a stable dose of tramadol hydrochloride extended-release tablets is achieved.

After stopping a CYP3A4 inhibitor, as the effects of the inhibitor decline, the tramadol plasma concentration will decrease [see CLINICAL PHARMACOLOGY], resulting in decreased opioid efficacy and possibly signs and symptoms of opioid withdrawal in patients who had developed physical dependence to tramadol.

If concomitant use is necessary, consider dosage reduction of tramadol hydrochloride extended-release tablets until stable drug effects are achieved. Inform patients and caregivers of this potential interaction, educate them on the signs and symptoms of seizures, serotonin syndrome, and signs of respiratory depression and sedation.

If a CYP3A4 inhibitor is discontinued, consider increasing the tramadol hydrochloride extended-release tablets dosage until stable drug effects are achieved and evaluate patients at frequent intervals for signs and symptoms of opioid withdrawal.

CYP3A4 Inducers

The concomitant use of tramadol hydrochloride extended-release tablets and CYP3A4 inducers such as rifampin, carbamazepine, phenytoin can decrease the plasma concentration of tramadol, [see CLINICAL PHARMACOLOGY], resulting in decreased efficacy or onset of a withdrawal syndrome in patients who have developed physical dependence to tramadol [see WARNINGS].

After stopping a CYP3A4 inducer, as the effects of the inducer decline, the tramadol plasma concentration will increase [see CLINICAL PHARMACOLOGY], which could increase or prolong both the therapeutic effects and adverse reactions, and may cause seizures and serotonin syndrome, and potentially fatal respiratory depression.

If concomitant use is necessary, consider increasing the tramadol hydrochloride extended-release tablets dosage until stable drug effects are achieved. Evaluate patients for signs of opioid withdrawal. If a CYP3A4 inducer is discontinued, consider tramadol hydrochloride extended-release tablets dose reduction and evaluate patients at frequent intervals for signs of respiratory depression and sedation.

Patients taking carbamazepine, a CYP3A4 inducer, may have a significantly reduced analgesic effect of tramadol. Because carbamazepine increases tramadol metabolism and because of the seizure risk associated with tramadol, concomitant administration of tramadol hydrochloride extended-release tablets and carbamazepine is not recommended.

Benzodiazepines and Other Central Nervous System (CNS) Depressants

Due to additive pharmacologic effect, the concomitant use of benzodiazepines or other CNS depressants such as alcohol, other sedatives/hypnotics, anxiolytics, tranquilizers, muscle relaxants, general anesthetics, antipsychotics, and other opioids, can increases the risk of respiratory depression, profound sedation, coma, and death.

Reserve concomitant prescribing of these drugs for use in patients for whom alternative treatment options are inadequate. Limit dosages and durations to the minimum required. Inform patients and caregivers of this potential interaction, educate them on the signs and symptoms of respiratory depression (including sedation). If concomitant use is warranted, consider recommending or prescribing an opioid overdose reversal agent. [see WARNINGS, DOSAGE AND ADMINISTRATION].

Serotonergic Drugs

The concomitant use of opioids with other drugs that affect the serotonergic neurotransmitter system such as selective serotonin reuptake inhibitors (SSRIs), serotonin and norepinephrine reuptake inhibitors (SNRIs), tricyclic antidepressants (TCAs), triptans, 5-HT3 receptor antagonists, drugs that affect the serotonin neurotransmitter system (e.g., mirtazapine, trazodone, tramadol), certain muscle relaxants (i.e., cyclobenzaprine, metaxalone), monoamine oxidase (MAO) inhibitors (those intended to treat psychiatric disorders and also others, such as linezolid and intravenous methylene blue) has resulted in serotonin syndrome.

If concomitant use is warranted, carefully observe the patient, particularly during treatment initiation and dose adjustment. Discontinue tramadol hydrochloride extended-release tablets if serotonin syndrome is suspected.

Monoamine Oxidase Inhibitors (MAOIs)

MAOI interactions with opioids may manifest as serotonin syndrome [see WARNINGS] or opioid toxicity (e.g., respiratory depression, coma) [see WARNINGS].

Do not use tramadol hydrochloride extended-release tablets in patients taking MAOIs or within 14 days of stopping such treatment.

Mixed Agonist/Antagonist and Partial Agonist Opioid Analgesics

Mixed agonist/antagonist and partial agonist opioid analgesics such as butorphanol, nalbuphine, pentazocine, buprenorphine, may reduce the analgesic effect of tramadol hydrochloride extended-release tablets and/or precipitate withdrawal symptoms. Advise patient to avoid concomitant use of these drugs.

Muscle Relaxants

Tramadol hydrochloride extended-release tablets may enhance the neuromuscular blocking action of skeletal muscle relaxants and produce an increased degree of respiratory depression.

Because respiratory depression may be greater than otherwise expected, decrease the dosage of tramadol hydrochloride extended-release tablets and/or the muscle relaxant as necessary. Due to the risk of respiratory depression with concomitant use of muscle relaxants and opioids, consider recommending or prescribing an opioid overdose reversal agent [see WARNINGS, DOSAGE AND ADMINISTRATION].

Diuretics

Opioids can reduce the efficacy of diuretics by inducing the release of antidiuretic hormone.

Evaluate patients for signs of diminished diuresis and/or effects on blood pressure and increase the dosage of the diuretic as needed.

Anticholinergic Drugs

The concomitant use of anticholinergic drugs may increase risk of urinary retention and/or severe constipation, which may lead to paralytic ileus.

Evaluate patients for signs of urinary retention or reduced gastric motility when tramadol hydrochloride extended-release tablets are used concomitantly with anticholinergic drugs.

Digoxin

Postmarketing surveillance has revealed rare reports of digoxin toxicity. Follow patients for signs of digoxin toxicity and adjust dosage of digoxin as needed.

Warfarin

Postmarketing surveillance of tramadol has revealed rare reports of alteration of warfarin effect, including elevation of prothrombin times. Monitor the prothrombin time of patients on warfarin for signs of an interaction and adjust the dosage of warfarin as needed.

Carcinogenesis, Mutagenesis and Impairment of Fertility

Carcinogenesis

Carcinogenicity assessment has been conducted in mice, rats and p53(+/-) heterozygous mice. A slight but statistically significant increase in two common murine tumors, pulmonary and hepatic, was observed in an NMRI mouse carcinogenicity study, particularly in aged mice. Mice were dosed orally up to 30 mg/kg in the drinking water (0.5 times the maximum recommended daily human dosage or MRHD) for approximately two years, although the study was not done with the Maximum Tolerated Dose. This finding is not believed to suggest risk in humans.

Mutagenesis

Tramadol was mutagenic in the presence of metabolic activation in the mouse lymphoma assay. Tramadol was not mutagenic in the in vitro bacterial reverse mutation assay using Salmonella and E. coli (Ames), the mouse lymphoma assay in the absence of metabolic activation, the in vitro chromosomal aberration assay, or the in vivo micronucleus assay in bone marrow.

Impairment of Fertility

No effects on fertility were observed for tramadol at oral dose levels up to 50 mg/kg in male rats and 75 mg/kg in female rats. These dosages are 1.2 and 1.8 times the maximum recommended human daily dose based on body surface area, respectively.

Infertility

Use of opioids for an extended period of time may cause reduced fertility in females and males of reproductive potential. It is not known whether these effects on fertility are reversible [see ADVERSE REACTIONS].

Pregnancy

Risk Summary

Use of opioid analgesics for an extended period of time during pregnancy may cause neonatal opioid withdrawal syndrome [see Warnings]. Available data with tramadol hydrochloride extended-release tablets in pregnant women are insufficient to inform a drug-associated risk for major birth defects and miscarriage.
In animal reproduction studies, tramadol administration during organogenesis decreased fetal weights and reduced ossification in mice, rats, and rabbits at 1.4, 0.6, and 3.6 times the maximum recommended human daily dosage (MRHD). Tramadol decreased pup body weight and increased pup mortality at 1.2 and 1.9 times the MRHD [see Data]. Based on animal data, advise pregnant women of the potential risk to a fetus.
The estimated background risk of major birth defects and miscarriage for the indicated population is unknown. All pregnancies have a background risk of birth defect, loss, or other adverse outcomes. In the U.S. general population, the estimated background risk of major birth defects and miscarriage in clinically recognized pregnancies is 2 to 4% and 15 to 20%, respectively.

Clinical Considerations

Fetal/Neonatal Adverse Reactions

Use of opioid analgesics for an extended period of time during pregnancy for medical or nonmedical purposes can result in physical dependence in the neonate and neonatal opioid withdrawal syndrome shortly after birth.
Neonatal opioid withdrawal syndrome presents as irritability, hyperactivity and abnormal sleep pattern, high pitched cry, tremor, vomiting, diarrhea, and failure to gain weight. The onset, duration, and severity of neonatal opioid withdrawal syndrome vary based on the specific opioid used, duration of use, timing and amount of last maternal use, and rate of elimination of the drug by the newborn. Observe newborns for symptoms and signs of neonatal opioid withdrawal syndrome and manage accordingly [see WARNINGS].
Neonatal seizures, neonatal withdrawal syndrome, fetal death and stillbirth have been reported with tramadol hydrochloride during post-approval use of tramadol hydrochloride extended release tablets.

Labor or Delivery

Opioids cross the placenta and may produce respiratory depression and psycho-physiologic effects in neonates. An opioid overdose reversal agent, such as naloxone or nalmefene, must be available for reversal of opioid-induced respiratory depression in the neonate. Tramadol hydrochloride extended-release tablets are not recommended for use in pregnant women during or immediately prior to labor, when use of shorter-acting analgesics or other analgesic techniques are more appropriate. Opioid analgesics, including tramadol hydrochloride extended-release tablets, can prolong labor through actions which temporarily reduce the strength, duration, and frequency of uterine contractions. However, this effect is not consistent and may be offset by an increased rate of cervical dilation, which tends to shorten labor. Monitor neonates exposed to opioid analgesics during labor for signs of excess sedation and respiratory depression.

Tramadol has been shown to cross the placenta. The mean ratio of serum tramadol in the umbilical veins compared to maternal veins was 0.83 for 40 women given tramadol during labor.

The effect of tramadol hydrochloride extended-release tablets, if any, on the later growth, development, and functional maturation of the child is unknown.

Data

Animal Data

Tramadol has been shown to be embryotoxic and fetotoxic in mice, (120 mg/kg), rats (25 mg/kg) and rabbits (75 mg/kg) at maternally toxic dosages, but was not teratogenic at these dose levels. These doses on a mg/m2 basis are 1.9, 0.8, and 4.9 times the maximum recommended human daily dosage (MRHD) for mouse, rat and rabbit, respectively.

No drug-related teratogenic effects were observed in progeny of mice (up to 140 mg/kg), rats (up to 80 mg/kg) or rabbits (up to 300 mg/kg) treated with tramadol by various routes. Embryo and fetal toxicity consisted primarily of decreased fetal weights, decreased skeletal ossification, and increased supernumerary ribs at maternally toxic dose levels. Transient delays in developmental or behavioral parameters were also seen in pups from rat dams allowed to deliver. Embryo and fetal lethality were reported only in one rabbit study at 300 mg/kg, a dose that would cause extreme maternal toxicity in the rabbit. The dosages listed for mouse, rat, and rabbit are 2.3, 2.6, and 19 times the MRHD, respectively.

Tramadol was evaluated in pre- and post-natal studies in rats. Progeny of dams receiving oral (gavage) dose levels of 50 mg/kg (1.6 times the MRHD) or greater had decreased weights, and pup survival was decreased early in lactation at 80 mg/kg (2.6 times the MRHD).

Nursing Mothers

Risk Summary

Tramadol hydrochloride extended-release tablets are not recommended for obstetrical preoperative medication or for post-delivery analgesia in nursing mothers because its safety in infants and newborns has not been studied.

Tramadol and its metabolite, O-desmethyl tramadol (M1), are present in human milk. There is no information on the effects of the drug on the breastfed infant or the effects of the drug on milk production. The M1 metabolite is more potent than tramadol in mu opioid receptor binding [see CLINICAL PHARMACOLOGY]. Published studies have reported tramadol and M1 in colostrum with administration of tramadol to nursing mothers in the early post-partum period. Women who are ultra-rapid metabolizers of tramadol may have higher than expected serum levels of M1, potentially leading to higher levels of M1 in breast milk that can be dangerous in their breastfed infants. In women with normal tramadol metabolism, the amount of tramadol secreted into human milk is low and dose-dependent. Because of the potential for serious adverse reactions, including excess sedation and respiratory depression in a breastfed infant, advise patients that breastfeeding is not recommended during treatment with tramadol hydrochloride extended-release tablets.

Clinical Considerations

Monitor infants exposed to tramadol hydrochloride extended-release tablets through breast milk for excess sedation and respiratory depression. Withdrawal symptoms can occur in breastfed infants when maternal administration of an opioid analgesic is stopped, or when breast-feeding is stopped.

Data

Following a single IV 100 mg dose of tramadol, the cumulative excretion in breast milk within 16 hours post dose was 100 mcg of tramadol (0.1% of the maternal dose) and 27 mcg of M1.

Pediatric Use

The safety and effectiveness of tramadol hydrochloride extended-release tablets in pediatric patients have not been established.
Life-threatening respiratory depression and death have occurred in children who received tramadol [see WARNINGS]. In some of the reported cases, these events followed tonsillectomy and/or adenoidectomy, and one of the children had evidence of being an ultra-rapid metabolizer of tramadol (i.e., multiple copies of the gene for cytochrome P450 isoenzyme 2D6 or high morphine concentrations). Children with sleep apnea may be particularly sensitive to the respiratory depressant effects of tramadol.

Because of the risk of life-threatening respiratory depression and death:

- Tramadol hydrochloride extended-release tablets are contraindicated for all children younger than 12 years of age [see CONTRAINDICATIONS].
- Tramadol hydrochloride extended-release tablets are contraindicated for post-operative management in pediatric patients younger than 18 years of age following tonsillectomy and/or adenoidectomy [see CONTRAINDICATIONS].
- Avoid the use of tramadol hydrochloride extended-release tablets in adolescents 12 to 18 years of age who have other risk factors that may increase their sensitivity to the respiratory depressant effects of tramadol unless the benefits outweigh the risks. Risk factors include conditions associated with hypoventilation, such as postoperative status, obstructive sleep apnea, obesity, severe pulmonary disease, neuromuscular disease, and concomitant use of other medications that cause respiratory depression.

Geriatric Use

In 12-week clinical trials, tramadol hydrochloride extended-release tablets were administered to 534 patients aged 65 years and older. Of those, 68 patients were 75 years of age and older. Comparable incidence rates of patients experiencing adverse events were observed for patients older than 65 years of age compared with younger patients (< 65 years of age), except constipation for which the incidence was higher in older patients. Tramadol hydrochloride extended-release tablets should be used with caution in patients older than 75 years of age [see CLINICAL PHARMACOLOGY, DOSAGE and ADMINISTRATION].

Respiratory depression is the chief risk for elderly patients treated with opioids, and has occurred after large initial doses were administered to patients who were not opioid-tolerant or when opioids were coadministered with other agents that depress respiration. Titrate the dosage of tramadol hydrochloride extended-release tablets slowly in geriatric patients and frequently reevaluate the patient for signs of central nervous system and respiratory depression [see Warnings].

Tramadol is known to be substantially excreted by the kidney, and the risk of adverse reactions to this drug may be greater in patients with impaired renal function. Because elderly patients are more likely to have decreased renal function, care should be taken in dose selection, and it may be useful to monitor renal function.

Hyponatremia

Hyponatremia (serum sodium < 135 mmol/L) has been reported with the use of tramadol, and many cases are severe (sodium level < 120 mmol/L). Most cases of hyponatremia occurred in females over the age of 65 and within the first week of therapy. In some reports, hyponatremia resulted from the syndrome of inappropriate antidiuretic hormone secretion (SIADH). Monitor for signs and symptoms of hyponatremia (e.g., confusion, disorientation), during treatment with tramadol hydrochloride extended-release tablets, especially during initiation of therapy. If signs and symptoms of hyponatremia are present, initiate appropriate treatment (e.g., fluid restriction) and discontinue tramadol hydrochloride extended-release tablets [see DOSAGE and ADMINISTRATION: Safe Reduction or Discontinuation of Tramadol Hydrochloride Extended-Release Tablets].

Hypoglycemia

Cases of tramadol-associated hypoglycemia have been reported, some resulting in hospitalization. In most cases, patients had predisposing risk factors (e.g. diabetes). If hypoglycemia is suspected, monitor blood glucose levels and consider drug discontinuation as appropriate [see DOSAGE and ADMINISTRATION: Safe Reduction or Discontinuation of Tramadol Hydrochloride Extended-Release Tablets].

ADVERSE REACTIONS

The following serious adverse reactions are described, or described in greater detail, in other sections:

- Addiction, Abuse, and Misuse (see WARNINGS)
- Life-Threatening Respiratory Depression (see WARNINGS)
- Ultra-Rapid Metabolism of Tramadol and Other Risk Factors for Life-Threatening Respiratory Depression in Children (see WARNINGS)
- Neonatal Opioid Withdrawal Syndrome (see WARNINGS)
- Interactions with Benzodiazepines or Other CNS Depressants (see WARNINGS)
- Opioid-Induced Hyperalgesia and Allodynia (see WARNINGS)
- Serotonin Syndrome (see WARNINGS)
- Seizures (see WARNINGS)
- Suicide (see WARNINGS)
- Adrenal Insufficiency (see WARNINGS)
- Severe Hypotension (see WARNINGS)
- Gastrointestinal Adverse Reactions (see WARNINGS)
- Hypersensitivity Reactions (see WARNINGS)
- Withdrawal (see WARNINGS)

Clinical Trials Experience

Because clinical trials are conducted under widely varying conditions, adverse reaction rates observed in the clinical trials of a drug cannot be directly compared to rates in the clinical trials of another drug and may not reflect the rates observed in practice.

Tramadol hydrochloride extended-release tablets were administered to a total of 2707 subjects (2406 patients and 301 healthy volunteers) during clinical studies, including four randomized double-blind studies (treatment ≥ 12 weeks) and two open-label long-term studies (treatment up to 12 months) in patients with moderate to severe pain due to osteoarthritis of the knee. A total of 844 patients were exposed to tramadol hydrochloride extended-release tablets for 12 weeks, 493 patients for 6 months and 243 patients for 12 months. Treatment emergent adverse events increased with dose from 100 mg to 300 mg in the three twelve-week, randomized, double-blind, placebo-controlled studies (Table 2).

Table 2. Percentage of Patients with Incidence of Adverse Events ≥ 2% from Three 12-week Placebo-Controlled Studies (MDT3-002, MDT3-003 and MDT3-005)
ADVERSE EVENTS (MEDRA Preferred Terms) | Tramadol Hydrochloride Extended-Release Tablets |  |  |  | Placebo
ADVERSE EVENTS (MEDRA Preferred Terms) | 100 mg | 200 mg | 300 mg | Total [*] | Placebo
ADVERSE EVENTS (MEDRA Preferred Terms) | N=216 | N=311 | N=530 | N=1095 | N=668
Nausea | 28 (13%) | 42 (14%) | 76 (14%) | 179 (16%) | 37 (6%)
Constipation | 21 (10%) | 36 (12%) | 52 (10%) | 140 (13%) | 26 (4%)
Dizziness | 16 (7%) | 28 (9%) | 52 (10%) | 106 (10%) | 18 (3%)
Somnolence | 11 (5%) | 22 (7%) | 23 (4%) | 77 (7%) | 12 (2%)
Vomiting | 7 (3%) | 16 (5%) | 31 (6%) | 58 (5%) | 4 (1%)
Pruritus | 9 (4%) | 15 (5%) | 18 (3%) | 51 (5%) | 7 (1%)
Headache | 10 (5%) | 9 (3%) | 15 (3%) | 41 (4%) | 21 (3%)
Sweating increased | 1 (0%) | 9 (3%) | 14 (3%) | 35 (3%) | 5 (1%)
Dry mouth | 7 (3%) | 13 (4%) | 6 (1%) | 32 (3%) | 8 (1%)
Fatigue | 6 (3%) | 7 (2%) | 9 (2%) | 26 (2%) | 6 (1%)
Anorexia | 4 (2%) | 4 (1%) | 10 (2%) | 25 (2%) | 2 (0%)
Vertigo | 2 (1%) | 3 (1%) | 6 (1%) | 21 (2%) | 3 (0%)
Insomnia | 2 (1%) | 6 (2%) | 9 (2%) | 18 (2%) | 8 (1%)

*Due to the difference in study design of MDT3-005, only the results of the double-blind phase of the study are presented and the dose specific results include maintenance period data only.

The majority of patients who experienced the most common adverse events (≥5%) reported mild to moderate symptoms. Less than 3% of adverse events were rated as severe. Overall, onset of these adverse events usually occurred within the first two weeks of treatment.

Adverse reactions with an incidence of 1.0% to <5.0%

Ear and labyrinth disorders: vertigo

Gastrointestinal disorders: abdominal pain, diarrhea, dry mouth, dyspepsia, upper abdominal pain

General disorders: fatigue, weakness

Investigations: weight decreased

Metabolism and nutrition disorders: anorexia

Musculoskeletal and connective tissue disorders: arthralgia

Nervous system disorders: headache, tremor

Psychiatric disorders: anxiety, insomnia

Skin and subcutaneous tissue disorders: pruritus, sweating increased

Vascular disorders: hot flushes

Adverse reactions with an incidence of <1.0%

Blood and lymphatic system disorders: anemia, thrombocytopenia

Cardiac disorders: bradycardia

Eye disorders: blurred vision, visual disturbance

Gastrointestinal disorders: abdominal discomfort, abdominal distension, abdominal tenderness, change in bowel habit, constipation aggravated, diverticulitis, diverticulum, dyspepsia aggravated, dysphagia, fecal impaction, gastric irritation, gastritis, gastrointestinal hemorrhage, gastrointestinal irritation, gastro-esophageal reflux disease, lower abdominal pain, pancreatitis aggravated, rectal hemorrhage, rectal prolapse, retching

General disorders: asthenia, malaise

Hepatobiliary disorders: biliary tract disorder, cholelithiasis

Immune system disorders: hypersensitivity

Investigations: alanine aminotransferase decreased, alanine aminotransferase increased, aspartate aminotransferase decreased, aspartate aminotransferase increased, blood amylase increased, blood creatinine increased, blood in stool, blood potassium abnormal, blood pressure increased gamma glutamyltransferase increased

Metabolism and nutrition disorders: appetite decreased, dehydration

Nervous system disorders: ataxia, disturbance in attention, dysarthria, gait abnormal, headache aggravated, mental impairment, sedation, seizure, sleep apnea syndrome, syncope, tremor

Psychiatric disorders: abnormal behavior, agitation, anxiety, confusion, depression, emotional disturbance, euphoric mood, indifference, irritability, libido decreased, nervousness, sleep disorder

Renal and urinary disorders: difficulty in micturition, urinary hesitation, urinary retention

Reproductive system and breast disorders: erectile dysfunction, sexual dysfunction

Respiratory, thoracic and mediastinal disorders: dyspnea

Skin and subcutaneous tissue disorders: allergic dermatitis, cold sweat, dermatitis, night sweats, pallor, generalized pruritus, urticaria

Vascular disorders: flushing, hypertension, hypotension, orthostatic hypotension

Postmarketing Experience

The following adverse reactions have been identified during post approval use of tramadol. Because these reactions are reported voluntarily from a population of uncertain size, it is not always possible to reliably estimate their frequency or establish a causal relationship to drug exposure.

- Serotonin syndrome: Cases of serotonin syndrome, a potentially life-threatening condition, have been reported during concomitant use of opioids with serotonergic drugs.
- Adrenal insufficiency: Cases of adrenal insufficiency have been reported with opioid use, more often following greater than one month of use.
- Anaphylaxis: Anaphylaxis has been reported with ingredients contained in tramadol hydrochloride extended-release tablets.
- Androgen deficiency: Cases of androgen deficiency have occurred with use of opioids for an extended period of time.
- Hyperalgesia and Allodynia: Cases of hyperalgesia and allodynia have been reported with opioid therapy of any duration [see Warnings]
- Hyponatremia: Cases of severe hyponatremia and/or SIADH have been reported in patients taking tramadol, most often in females over the age of 65, and within the first week of therapy [see PRECAUTIONS].
- Hypoglycemia: Cases of hypoglycemia have been reported in patients taking tramadol. Most reports were in patients with predisposing risk factors, including diabetes or renal insufficiency, or in elderly patients [see PRECAUTIONS].
- Opioid-induced esophageal dysfunction (OIED): Cases of OIED have been reported in patients taking opioids, and may occur more frequently in patients taking higher doses of opioids, and/or in patients taking opioids longer term [see WARNINGS].

Adverse Reactions from Observational Studies

A prospective, observational cohort study estimated the risks of addiction, abuse, and misuse in patients initiating long-term use of Schedule II opioid analgesics between 2017 and 2021. Study participants included in one or more analyses had been enrolled in selected insurance plans or health systems for at least one year, were free of at least one outcome at baseline, completed a minimum number of follow-up assessments, and either: 1) filled multiple extended-release/long-acting opioid analgesic prescriptions during a 90 day period (n=978); or 2) filled any Schedule II opioid analgesic prescriptions covering at least 70 of 90 days (n=1,244). Those included also had no dispensing of the qualifying opioids in the previous 6 months.

Over 12 months:
• approximately 1% to 6% of participants across the two cohorts newly met criteria for addiction, as assessed with two validated interview-based measures of moderate-to-severe opioid use disorder based on Diagnostic and Statistical Manual of Mental Disorders, Fifth Edition (DSM-5) criteria, and
• approximately 9% and 22% of participants across the two cohorts newly met criteria for prescription opioid abuse and misuse [defined in DRUG ABUSE AND DEPENDENCE], respectively, as measured with a validated self-reported instrument.

A retrospective, observational cohort study estimated the risk of opioid-involved overdose or opioid overdose-related death in patients with new long-term use of Schedule II opioid analgesics from 2006 through 2016 (n=220,249). Included patients had been enrolled in either one of two commercial insurance programs, one managed care program, or one Medicaid program for at least 9 months. New long-term use was defined as having Schedule II opioid analgesic prescriptions covering at least 70 days’ supply over the 3 months prior to study entry and none during the preceding 6 months. Patients were excluded if they had an opioid-involved overdose in the 9 months prior to study entry. Overdose was measured using a validated medical code-based algorithm with linkage to the National Death Index database. The 5-year cumulative incidence estimates for opioid-involved overdose or opioid overdose-related death ranged from approximately 1.5% to 4% across study sites, counting only the first event during follow-up. Approximately 17% of first opioid overdoses observed over the entire study period (5-11 years, depending on the study site) were fatal. Higher baseline opioid dose was the strongest and most consistent predictor of opioid-involved overdose or opioid overdose-related death. Study exclusion criteria may have selected patients at lower risk of overdose, and substantial loss to follow-up (approximately 80%) also may have biased estimates.

The risk estimates from the studies described above may not be generalizable to all patients receiving opioid analgesics, such as those with exposures shorter or longer than the duration evaluated in the studies.

DRUG ABUSE AND DEPENDENCE

Controlled Substance

Tramadol hydrochloride extended-release tablets contain tramadol, a Schedule IV controlled substance.

Abuse

Tramadol hydrochloride extended-release tablets contain tramadol, a substance with high potential for misuse and abuse, which can lead to the development of substance use disorder, including addiction [see Warnings].

Misuse is the intentional use, for therapeutic purposes, of a drug by an individual in a way other than prescribed by a healthcare provider or for whom it was not prescribed.

Abuse is the intentional, non-therapeutic use of a drug, even once, for its desirable psychological or physiological effects.

Drug addiction is a cluster of behavioral, cognitive, and physiological phenomena that may include a strong desire to take the drug, difficulties in controlling drug use (e.g., continuing drug use despite harmful consequences, giving a higher priority to drug use than other activities and obligations), and possible tolerance or physical dependence.

Misuse and abuse of tramadol hydrochloride extended-release tablets increases risk of overdose, which may lead to central nervous system and respiratory depression, hypotension, seizures, and death. The risk is increased with concurrent use of tramadol hydrochloride extended-release tablets with alcohol and/or other CNS depressants. Abuse of and addiction to opioids in some individuals may not be accompanied by concurrent tolerance and symptoms of physical dependence. In addition, abuse of opioids can occur in the absence of addiction.

All patients treated with opioids require careful and frequent re-evaluation for signs of misuse, abuse, and addiction, because use of opioid analgesic products carries the risk of addiction even under appropriate medical use. Patients at high risk of tramadol hydrochloride extended-release tablets abuse include those with a history of prolonged use of any opioids, including products containing tramadol, those with a history of drug or alcohol abuse, or those who use tramadol hydrochloride extended-release tablets in combination with other abused drugs.

“Drug-seeking” behavior is very common in persons with substance use disorders. Drug-seeking tactics include emergency calls or visits near the end of office hours, refusal to undergo appropriate examination, testing, or referral, repeated “loss” of prescriptions, tampering with prescriptions, and reluctance to provide prior medical records or contact information for other treating healthcare provider(s). “Doctor shopping” (visiting multiple prescribers to obtain additional prescriptions) is common among people who abuse drugs and people with substance use disorder. Preoccupation with achieving adequate pain relief can be appropriate behavior in a patient with inadequate pain control.

Tramadol hydrochloride extended-release tablets, like other opioids, can be diverted for nonmedical use into illicit channels of distribution. Careful record-keeping of prescribing information, including quantity, frequency, and renewal requests, as required by state and federal law, is strongly advised.

Proper assessment of the patient, proper prescribing practices, periodic reevaluation of therapy, and proper dispensing and storage are appropriate measures that help to limit abuse of opioid drugs.

Risks Specific to Abuse of Tramadol Hydrochloride Extended-Release Tablets

Abuse of tramadol hydrochloride extended-release tablets poses a risk of overdose and death.

Tramadol hydrochloride extended-release tablets are approved for oral use only. Inappropriate intravenous, intramuscular, or subcutaneous use of tramadol hydrochloride extended-release tablets can result in local tissue necrosis, infection, pulmonary granulomas, increased risk of endocarditis and valvular heart injury, embolism, and death.

Parenteral drug abuse is commonly associated with transmission of infectious diseases such as hepatitis and HIV.

Dependence

Both tolerance and physical dependence can develop during use of opioid therapy.

Tolerance is a physiological state characterized by a reduced response to a drug after repeated administration (i.e., a higher dose of a drug is required to produce the same effect that was once obtained at a lower dose).

Physical dependence is a state that develops as a result of a physiological adaptation in response to repeated drug use, manifested by withdrawal signs and symptoms after abrupt discontinuation or a significant dose reduction of a drug.

Withdrawal may be precipitated through the administration of drugs with opioid antagonist activity (e.g., naloxone, nalmefene), mixed agonist/antagonist analgesics (e.g., pentazocine, butorphanol, nalbuphine), or partial agonists (e.g., buprenorphine). Physical dependence may not occur to a clinically significant degree until after several days to weeks of continued use.

Do not rapidly reduce or abruptly discontinue tramadol hydrochloride extended-release tablets in a patient physically dependent on opioids. Rapid reduction or abrupt discontinuation of tramadol hydrochloride extended-release tablets in a patient physically dependent on opioids may lead to serious withdrawal symptoms, uncontrolled pain, and suicide. Rapid reduction or abrupt discontinuation has also been associated with attempts to find other sources of opioid analgesics, which may be confused with drug-seeking for abuse.

When discontinuing tramadol hydrochloride extended-release tablets, gradually taper the dosage using a patient-specific plan that considers the following: the dose of tramadol hydrochloride extended-release tablets the patient has been taking, the duration of treatment, and the physical and psychological attributes of the patient. To improve the likelihood of a successful taper and minimize withdrawal symptoms, it is important that the opioid tapering schedule is agreed upon by the patient. In patients taking opioids for an extended period of time at high doses, ensure that a multimodal approach to pain management, including mental health support (if needed), is in place prior to initiating an opioid analgesic taper [see Dosage and Administration, and Warnings].

Infants born to mothers physically dependent on opioids will also be physically dependent and may exhibit respiratory difficulties and withdrawal signs [see Precautions; Pregnancy].

OVERDOSAGE

Clinical Presentation

Acute overdosage with tramadol hydrochloride extended-release tablets can be manifested by respiratory depression, somnolence progressing to stupor or coma, skeletal muscle flaccidity, cold and clammy skin, constricted pupils, and, in some cases, pulmonary edema, bradycardia, hypotension, partial or complete airway obstruction, atypical snoring, and death. Marked mydriasis rather than miosis may be seen with hypoxia in overdose situations [see CLINICAL PHARMACOLOGY]. Toxic leukoencephalopathy has been reported after opioid overdose and can present hours, days, or weeks after apparent recovery from the initial intoxication.

Treatment of Overdose

In case of overdose, priorities are the reestablishment of a patent and protected airway and institution of assisted or controlled ventilation, if needed. Employ other supportive measures (including oxygen and vasopressors) in the management of circulatory shock and pulmonary edema as indicated. Cardiac arrest or arrhythmias will require advanced life-support measures.

For clinically significant respiratory or circulatory depression secondary to tramadol overdose, administer an opioid overdose reversal agent such as naloxone or nalmefene.

While an opioid overdose reversal agent will reverse some (but not all) symptoms caused by overdosage with tramadol, the risk of seizures is also increased with reversal agent administration. In animals, convulsions following the administration of toxic doses of tramadol hydrochloride extended-release tablets could be suppressed with barbiturates or benzodiazepines but were increased with naloxone. Naloxone administration did not change the lethality of an overdose in mice. Hemodialysis is not expected to be helpful in an overdose because it removes less than 7% of the administered dose in a 4-hour dialysis period.

Because the duration of opioid reversal is expected to be less than the duration of action of tramadol in tramadol hydrochloride extended-release tablets, carefully monitor the patient until spontaneous respiration is reliably reestablished. Tramadol hydrochloride extended-release tablets will continue to release tramadol and add to the tramadol load for 24 to 48 hours or longer following ingestion, necessitating prolonged monitoring. If the response to an opioid overdose reversal agent is suboptimal or only brief in nature, administer additional reversal agent as directed by the product’s prescribing information.

In an individual physically dependent on opioids, administration of the recommended usual dosage of the opioid overdose reversal agent will precipitate an acute withdrawal syndrome. The severity of the withdrawal symptoms experienced will depend on the degree of physical dependence and the dose of the reversal agent administered. If a decision is made to treat serious respiratory depression in the physically dependent patient, administration of the reversal agent should be initiated with care and by titration with smaller than usual doses of thereversal agent.

DOSAGE AND ADMINISTRATION

Important Dosage and Administration Instructions

- Tramadol hydrochloride extended-release tablets should be prescribed only by healthcare professionals who are knowledgeable about the use of extended-release/long-acting opioids and how to mitigate the associated risks.
- Do not use tramadol hydrochloride extended-release tablets concomitantly with other tramadol products [see WARNINGS].
- Do not administer tramadol hydrochloride extended-release tablets at a dose exceeding 300 mg per day.
- Use the lowest effective dosage for the shortest duration of time consistent with individual patient treatment goals [see Warnings]. Because the risk of overdose increases as opioid doses increase, reserve titration to higher doses of tramadol hydrochloride extended-release tablets for patients in whom lower doses are insufficiently effective and in whom the expected benefits of using a higher dose opioid clearly outweigh the substantial risks.
  - Initiate the dosing regimen for each patient individually, taking into account the patient’s underlying cause and severity of pain, prior analgesic treatment and response, and risk factors for addiction, abuse, and misuse [see Warnings]
- Respiratory depression can occur at any time during opioid therapy, especially when initiating and following dosage increases with tramadol hydrochloride extended-release tablets. Consider this risk when selecting an initial dose and when making dose adjustments [see Warnings].
- Tramadol hydrochloride extended-release tablets should be taken once daily, at approximately the same time every day.
- Instruct patients to swallow tramadol hydrochloride extended-release tablets whole [see PRECAUTIONS; Information for Patients], and to take it with liquid. Crushing, chewing, splitting, or dissolving tramadol hydrochloride extended-release tablets will result in uncontrolled delivery of tramadol and can lead to overdose or death [see WARNINGS].
- Tramadol hydrochloride extended-release tablets may be taken without regard to food, it is recommended that it be taken in a consistent manner [see CLINICAL PHARMACOLOGY].

Patient Access to an Opioid Overdose Reversal Agent for the Emergency Treatment of Opioid Overdose

Inform patients and caregivers about opioid overdose reversal agents (e.g., naloxone, nalmefene). Discuss the importance of having access to an opioid overdose reversal agent, especially if the patient has risk factors for overdose (e.g., concomitant use of CNS depressants, a history of opioid use disorder, or prior opioid overdose) or if there are household members (including children) or other close contacts at risk for accidental ingestion or opioid overdose. The presence of risk factors for overdose should not prevent the management of pain in any patient [see WARNINGS; Addiction, Abuse, and Misuse; Life-Threatening Respiratory Depression; Risks from Concomitant Use with Benzodiazepines or Other CNS Depressants].

Discuss the options for obtaining an opioid overdose reversal agent (e.g., prescription, over-the-counter, or as part of a community-based program).

There are important differences among the opioid overdose reversal agents, such as route of administration, product strength, approved patient age range, and pharmacokinetics. Be familiar with these differences, as outlined in the approved labeling for those products, prior to recommending or prescribing such an agent.

Initial Dosage

It is safer to underestimate a patient’s 24-hour tramadol requirements and provide rescue medication (e.g., immediate-release opioid) than to overestimate the 24-hour tramadol dosage and manage an adverse reaction due to an overdose. While useful tables of opioid equivalents are readily available, there is inter-patient variability in the potency of opioid drugs and opioid formulations. Frequently reevaluate patients for signs and symptoms of opioid withdrawal and for signs of oversedation/toxicity after converting patients to Tramadol Hydrochloride Extended-Release Tablets.

Use of Tramadol Hydrochloride Extended-Release Tablets
The initial dose of tramadol hydrochloride extended-release tablets is 100 mg once daily.

Patients Currently on Tramadol Immediate-Release (IR) Products

Calculate the 24-hour tramadol IR dose and initiate a total daily dose of tramadol hydrochloride extended-release tablets rounded down to the next lower 100 mg increment. The dose should be taken once daily. The dose may subsequently be individualized according to patient need.

Due to limitations in flexibility of dose selection with tramadol hydrochloride extended-release tablets, some patients maintained on tramadol IR products may not be able to convert to tramadol hydrochloride extended-release tablets.

Conversion from Other Opioid Analgesics to Tramadol Hydrochloride Extended-Release Tablets

When tramadol hydrochloride extended-release tablets therapy is initiated, discontinue all opioid analgesics other than those used on an as needed basis for breakthrough pain when appropriate. There are no established conversion ratios for conversion from other opioids to tramadol hydrochloride extended-release tablets defined by clinical trials. It is safer to underestimate a patient’s 24-hour tramadol requirements and provide rescue medication (e.g., immediate-release opioid) than to overestimate the 24-hour tramadol dosage and manage an adverse reaction due to an overdose. While useful tables of opioid equivalents are readily available, there is inter-patient variability in the potency of opioid drugs and opioid formulations. Frequently reevaluate patients for signs and symptoms of opioid withdrawal and for signs of oversedation/toxicity after converting patients to Tramadol Hydrochloride Extended-Release Tablets.

Use of Tramadol Hydrochloride Extended-Release Tablets
The initial dose of tramadol hydrochloride extended-release tablets is 100 mg once daily.

Titration and Maintenance of Therapy

Individually titrate tramadol hydrochloride extended-release tablets by 100 mg every five days to a dose that provides adequate analgesia and minimizes adverse reactions. The maximum daily dose of tramadol hydrochloride extended-release tablets is 300 mg per day.

Continually reevaluate patients receiving tramadol hydrochloride extended-release tablets to assess the maintenance of pain control and, signs and symptoms of opioid withdrawal, and other adverse reactions as well as to reassess for the development of addiction, abuse, or misuse [see Warnings and Withdrawal]. Frequent communication is important among the prescriber, other members of the healthcare team, the patient, and the caregiver/family during periods of changing analgesic requirements, including initial titration. During use of opioid therapy for an extended period of time, periodically reassess the continued need for the use of opioid analgesics.

Patients who experience breakthrough pain may require a dosage adjustment of tramadol hydrochloride extended-release tablets, or may need rescue medication with an appropriate dose of an immediate-release analgesic.

If the level of pain increases after dosage stabilization, attempt to identify the source of increased pain before increasing the tramadol hydrochloride extended-release tablets dosage.

If after increasing the dosage, unacceptable opioid-related adverse reactions are observed (including an increase in pain after dosage increase), consider reducing the dosage [see Warnings]. Adjust the dosage to obtain an appropriate balance between management of pain and opioid-related adverse reactions.

Safe Reduction or Discontinuation of Tramadol Hydrochloride Extended-Release Tablets

Do not rapidly reduce or abruptly discontinue tramadol hydrochloride extended-release tablets in patients who may be physically dependent on opioids. Rapid reduction or abrupt discontinuation of opioid analgesics in patients who are physically dependent on opioids has resulted in serious withdrawal symptoms, uncontrolled pain, and suicide. Rapid reduction or abrupt discontinuation has also been associated with attempts to find other sources of opioid analgesics, which may be confused with drug-seeking for abuse. Patients may also attempt to treat their pain or withdrawal symptoms with illicit opioids, such as heroin, and other substances.

When a decision has been made to decrease the dose or discontinue therapy in an opioid-dependent patient taking tramadol hydrochloride extended-release tablets, there are a variety of factors that should be considered, including the total daily dose of opioid (including tramadol hydrochloride extended-release tablets) the patient has been taking, the duration of treatment, the type of pain being treated, and the physical and psychological attributes of the patient. It is important to ensure ongoing care of the patient and to agree on an appropriate tapering schedule and follow-up plan so that patient and provider goals and expectations are clear and realistic. When opioid analgesics are being discontinued due to a suspected substance use disorder, evaluate and treat the patient, or refer for evaluation and treatment of the substance use disorder. Treatment should include evidence-based approaches, such as medication assisted treatment of opioid use disorder. Complex patients with co-morbid pain and substance use disorders may benefit from referral to a specialist.

There are no standard opioid tapering schedules that are suitable for all patients. Good clinical practice dictates a patient-specific plan to taper the dose of the opioid gradually. For patients on tramadol hydrochloride extended-release tablets who are physically opioid-dependent, initiate the taper by a small enough increment (e.g., no greater than 10% to 25% of the total daily dose) to avoid withdrawal symptoms, and proceed with dose lowering at an interval of every 2 to 4 weeks. Patients who have been taking opioids for briefer periods of time may tolerate a more rapid taper.

It may be necessary to provide the patient with lower dosage strengths to accomplish a successful taper. Reassess the patient frequently to manage pain and withdrawal symptoms, should they emerge. Common withdrawal symptoms include restlessness, lacrimation, rhinorrhea, yawning, perspiration, chills, myalgia, and mydriasis. Other signs and symptoms also may develop, including irritability, anxiety, backache, joint pain, weakness, abdominal cramps, insomnia, nausea, anorexia, vomiting, diarrhea, or increased blood pressure, respiratory rate, or heart rate. If withdrawal symptoms arise, it may be necessary to pause the taper for a period of time or raise the dose of the opioid analgesic to the previous dose, and then proceed with a slower taper. In addition, evaluate patients for any changes in mood, emergence of suicidal thoughts, or use of other substances.

When managing patients taking opioid analgesics, particularly those who have been treated for an extended period of time, and/or with high doses for chronic pain, ensure that a multimodal approach to pain management, including mental health support (if needed), is in place prior to initiating an opioid analgesic taper. A multimodal approach to pain management may optimize the treatment of chronic pain, as well as assist with the successful tapering of the opioid analgesic [see WARNINGS/ Withdrawal, DRUG ABUSE and DEPENDENCE].

HOW SUPPLIED

Tramadol hydrochloride extended-release tablets, USP are available as follows:

100 mg: White, round shape, biconvex, beveled edge, coated tablet with release portal on the center of the tablet on any one side, imprinted “531” with black ink on one side and plain on other side.

Bottles of 30’s with Child Resistant Cap…………..….NDC 47335-531-83

Bottles of 100’s with Child Resistant Cap………….....NDC 47335-531-88

Bottles of 100’s with Non Child Resistant Cap…….....NDC 47335-531-08

Bottles of 1000’s with Non Child Resistant Cap……...NDC 47335-531-18

200 mg: White, round shape, biconvex, beveled edge, coated tablet with release portal on the center of the tablet on any one side, imprinted “533” with black ink on one side and plain on other side.

Bottles of 30’s with Child Resistant Cap………………NDC 47335-533-83

Bottles of 100’s with Child Resistant Cap……………..NDC 47335-533-88

Bottles of 100’s with Non Child Resistant Cap………..NDC 47335-533-08

Bottles of 1000’s with Non Child Resistant Cap……....NDC 47335-533-18

300 mg: White, round shape, biconvex, beveled edge, coated tablet with release portal on the center of the tablet on any one side, imprinted “537” with black ink on one side and plain on other side.

Bottles of 30’s with Child Resistant Cap…...................NDC 47335-537-83

Bottles of 100’s with Child Resistant Cap….................NDC 47335-537-88

Bottles of 100’s with Non Child Resistant Cap….........NDC 47335-537-08

Bottles of 1000’s with Non Child Resistant Cap….......NDC 47335-537-18

Store at 20° to 25°C (68° to 77°F); excursions permitted between 15° and 30°C (59° and 86°F) [see USP Controlled Room Temperature].

Dispense in a tight, light resistant container.

Warning: keep out of reach of children.

Store tramadol hydrochloride extended-release tablets securely and dispose of properly [see PRECAUTIONS/ Information for Patients].

Medication Guide

Tramadol Hydrochloride (tram a dol hye droe klor ide)

Extended-Release Tablets, USP, C-IV

Tramadol hydrochloride extended-release tablets are:

- A strong prescription pain medicine that contains an opioid (narcotic) that is used to manage severe and persistent pain that requires an extended treatment period with a daily opioid pain medicine when other pain medicines do not treat your pain well enough or you cannot tolerate them.
- A long-acting (extended-release) opioid pain medicine that can put you at risk for overdose and death. Even if you take your dose correctly as prescribed you are at risk for opioid addiction, abuse, and misuse that can lead to death.
- Not to be taken on an “as needed” basis.

Important information about tramadol hydrochloride extended-release tablets:

- Get emergency help or call 911 right away if you take too many tramadol hydrochloride extended-release tablets (overdose). When you first start taking tramadol hydrochloride extended-release tablets, when your dose is changed, or if you take too many (overdose), serious or life-threatening breathing problems that can lead to death may occur. Ask your healthcare provider about medicines like naloxone or nalmefene that can be used in an emergency to reverse an opioid overdose.
- Taking tramadol hydrochloride extended-release tablets with other opioid medicines, benzodiazepines, gabapentinoids (gabapentin or pregabalin), alcohol, or other central nervous system depressants (including street drugs) can cause severe drowsiness, decreased awareness, breathing problems, coma, and death.
- Never give anyone else your tramadol hydrochloride extended-release tablets. They could die from taking them. Selling or giving away tramadol hydrochloride extended-release tablets is against the law.
- Store tramadol hydrochloride extended-release tablets securely, out of sight and reach of children, and in a location not accessible by others, including visitors to the home.

Important Information Guiding Use in Pediatric Patients:

- Do not give tramadol hydrochloride extended-release tablets to a child younger than 12 years of age.
- Do not give tramadol hydrochloride extended-release tablets to a child younger than 18 years of age after surgery to remove the tonsils and/or adenoids.
- Avoid giving tramadol hydrochloride extended-release tablets to children between 12 to 18 years of age who have risk factors for breathing problems such as obstructive sleep apnea, obesity, or underlying lung problems.

Do not take tramadol hydrochloride extended-release tablets if you have:

- severe asthma, trouble breathing, or other lung problems.
- a bowel blockage or have narrowing of the stomach or intestines.

Before taking tramadol hydrochloride extended-release tablets, tell your healthcare provider if you have a history of:

- head injury, seizures ● liver, kidney, thyroid problems
- problems urinating ● pancreas or gallbladder problems
- abuse of street or prescription drugs, alcohol addiction, opioid overdose, or mental health problems.

Tell your healthcare provider if you:

- notice your pain getting worse. If your pain gets worse after you take tramadol hydrochloride extended-release tablets, do not take more of tramadol hydrochloride extended-release tablets without first talking to your healthcare provider. Talk to your healthcare provider if the pain that you have increases, if you feel more sensitive to pain, or if you have new pain after taking tramadol hydrochloride extended-release tablets.
- Are pregnant or planning to become pregnant. Use of tramadol hydrochloride extended-release tablets for an extended period of time during pregnancy can cause withdrawal symptoms in your newborn baby that could be life-threatening if not recognized and treated.
- breastfeeding. Not recommended. It may harm your baby.
- living in a household where there are small children or someone who has abused street or prescription drugs
- taking prescription or over-the-counter medicines, vitamins, or herbal supplements. Taking tramadol hydrochloride extended-release tablets with certain other medicines can cause serious side effects that could lead to death.

When taking tramadol hydrochloride extended-release tablets:

- Do not change your dose. Take tramadol hydrochloride extended-release tablets exactly as prescribed by your healthcare provider. Use the lowest dose possible for the shortest time needed.
- Take your prescribed dose once a day at the same time every day. Do not take more than your prescribed dose. If you miss a dose, take your next dose at your usual time.
- Swallow tramadol hydrochloride extended-release tablets whole. Do not cut, break, chew, crush, dissolve, snort, or inject tramadol hydrochloride extended-release tablets because this may cause you to overdose and die.
- Call your healthcare provider if the dose you are taking does not control your pain.
- Do not stop taking tramadol hydrochloride extended-release tablets without talking to your healthcare provider.
- Dispose of expired, unwanted, or unused tramadol hydrochloride extended-release tablets by taking your drug to an authorized DEA-registered collector or drug take-back program. If one is not available, you can dispose of tramadol hydrochloride extended-release tablets by mixing the product with dirt, cat litter, or coffee grounds; placing the mixture in a sealed plastic bag, and throwing the bag in your trash. Visit www.fda.gov/drugdisposal for additional information on disposal of unused medicines.

While taking tramadol hydrochloride extended-release tablets DO NOT:

- Drive or operate heavy machinery, until you know how tramadol hydrochloride extended-release tablets affect you. Tramadol hydrochloride extended-release tablets can make you sleepy, dizzy, or lightheaded.
- Drink alcohol or use prescription or over-the-counter medicines that contain alcohol. Using products containing alcohol during treatment with tramadol hydrochloride extended-release tablets may cause you to overdose and die.

The possible side effects of tramadol hydrochloride extended-release tablets:

- constipation, nausea, sleepiness, vomiting, tiredness, headache, dizziness, abdominal pain, seizure. Call your healthcare provider if you have any of these symptoms and they are severe.

Get emergency medical help or call 911 right away if you have:

- trouble breathing, shortness of breath, fast heartbeat, chest pain, swelling of your face, tongue, or throat, extreme drowsiness, light-headedness when changing positions, feeling faint, agitation, high body temperature, trouble walking, stiff muscles, or mental changes such as confusion.

These are not all the possible side effects of tramadol hydrochloride extended-release tablets. Call your healthcare provider for medical advice about side effects. You may report side effects to FDA at 1-800-FDA-1088. For more information go to dailymed.nlm.nih.gov or call 1-800-818-4555

This Medication Guide has been approved by the U.S. Food and Drug Administration.

Distributed by:

Sun Pharmaceutical Industries, Inc.

Cranbury, NJ 08512

Manufactured by:

Sun Pharmaceutical Industries Limited

Halol-Baroda Highway,

Halol-389 350, Gujarat, India.

Revised. 12/2025

PRINCIPAL DISPLAY PANEL - Label 100 mg

NDC 47335-531-83
(Once Daily)
Tramadol Hydrochloride Extended-release Tablets, USP CIV
100 mg
The tablets should be swallowed whole with liquid and not split, chewed, dissolved or crushed.

PHARMACIST: Dispense with Medication Guide to each patient.
Rx only
30 Tablets
SUN PHARMA

PRINCIPAL DISPLAY PANEL - Label 200 mg

NDC 47335-533-83
(Once Daily)
Tramadol Hydrochloride Extended-release Tablets, USP CIV
200 mg
The tablets should be swallowed whole with liquid and not split, chewed, dissolved or crushed.

PHARMACIST: Dispense with Medication Guide to each patient.

Rx only
30 Tablets
SUN PHARMA

PRINCIPAL DISPLAY PANEL - Label 300 mg

NDC 47335-537-83
(Once Daily)
Tramadol Hydrochloride Extended-release Tablets, USP CIV
300 mg
The tablets should be swallowed whole with liquid and not split, chewed, dissolved or crushed.

PHARMACIST: Dispense with Medication Guide to each patient.
Rx only
30 Tablets
SUN PHARMA